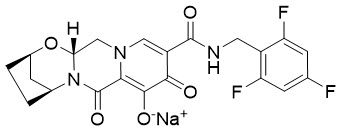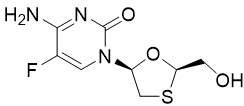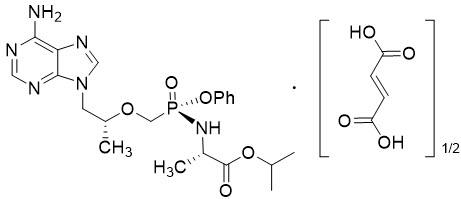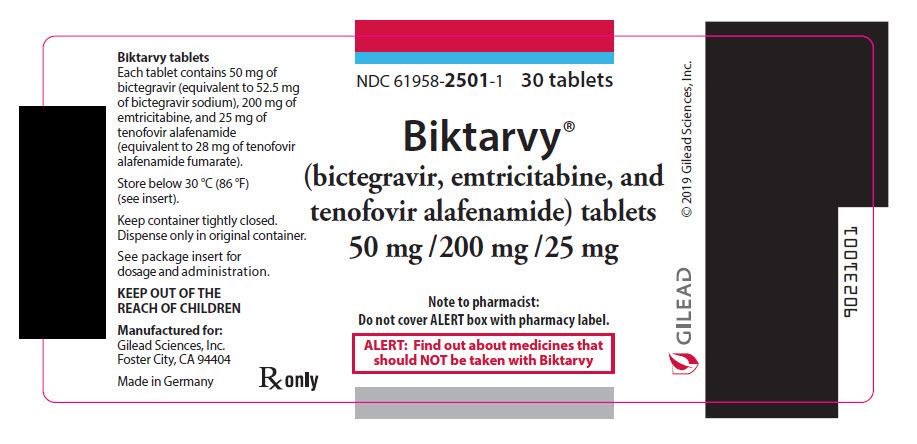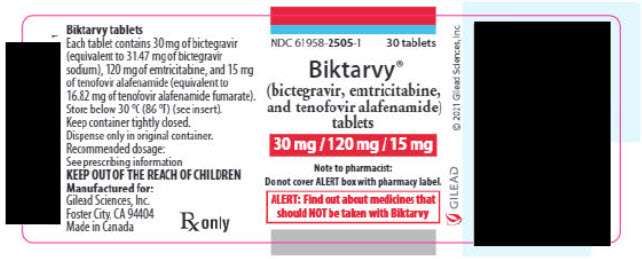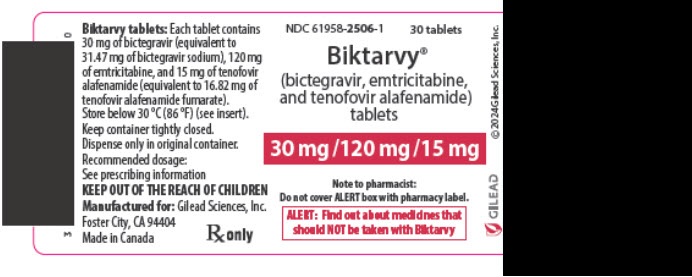 DRUG LABEL: Biktarvy
NDC: 61958-2501 | Form: TABLET
Manufacturer: Gilead Sciences, Inc.
Category: prescription | Type: HUMAN PRESCRIPTION DRUG LABEL
Date: 20260212

ACTIVE INGREDIENTS: BICTEGRAVIR SODIUM 50 mg/1 1; EMTRICITABINE 200 mg/1 1; TENOFOVIR ALAFENAMIDE FUMARATE 25 mg/1 1
INACTIVE INGREDIENTS: MICROCRYSTALLINE CELLULOSE; CROSCARMELLOSE SODIUM; MAGNESIUM STEARATE; WATER; POLYVINYL ALCOHOL, UNSPECIFIED; TITANIUM DIOXIDE; POLYETHYLENE GLYCOL, UNSPECIFIED; TALC; FERROSOFERRIC OXIDE; FERRIC OXIDE RED

HIGHLIGHTS OF PRESCRIBING INFORMATION

These highlights do not include all the information needed to use BIKTARVY safely and effectively. See full prescribing information for BIKTARVY.
BIKTARVY® (bictegravir, emtricitabine, and tenofovir alafenamide) tablets, for oral use
Initial U.S. Approval: 2018

WARNING: POST TREATMENT ACUTE EXACERBATION OF HEPATITIS B

See full prescribing information for complete boxed warning.

Severe acute exacerbations of hepatitis B have been reported in patients with HIV-1 and HBV who have discontinued products containing emtricitabine (FTC) and/or tenofovir disoproxil fumarate (TDF), and may occur with discontinuation of BIKTARVY. Closely monitor hepatic function in these patients. If appropriate, anti-hepatitis B therapy may be warranted. (5.1)

RECENT MAJOR CHANGES

Indications and Usage (1) | 07/2025

1 INDICATIONS AND USAGE

BIKTARVY is a three-drug combination of bictegravir (BIC), a human immunodeficiency virus type 1 (HIV-1) integrase strand transfer inhibitor (INSTI), and emtricitabine (FTC) and tenofovir alafenamide (TAF), both HIV-1 nucleoside analog reverse transcriptase inhibitors (NRTIs), and is indicated as a complete regimen for the treatment of HIV-1 infection in adults and pediatric patients weighing at least 14 kg:

- with no antiretroviral treatment history or
- with an antiretroviral treatment history and not virologically suppressed, with no known or suspected substitutions associated with resistance to the integrase strand inhibitor class, emtricitabine, or tenofovir, or
- to replace the current antiretroviral regimen in those who are virologically suppressed (HIV-1 RNA less than 50 copies per mL) on a stable antiretroviral regimen with no known or suspected substitutions associated with resistance to bictegravir or tenofovir. (1)

2 DOSAGE AND ADMINISTRATION

- Testing: Prior to or when initiating BIKTARVY test for hepatitis B virus infection. Prior to or when initiating BIKTARVY, and during treatment, assess serum creatinine, estimated creatinine clearance, urine glucose, and urine protein in all patients as clinically appropriate. In patients with chronic kidney disease, also assess serum phosphorus. (2.1)
- Recommended dosage in adults and pediatric patients weighing at least 25 kg, or virologically-suppressed adults with estimated creatinine clearance below 15 mL/min receiving chronic hemodialysis: One tablet containing 50 mg BIC, 200 mg FTC, and 25 mg TAF taken once daily with or without food. (2.2)
- Recommended dosage in pediatric patients weighing at least 14 kg to less than 25 kg: One tablet containing 30 mg BIC, 120 mg FTC, and 15 mg TAF taken once daily with or without food. (2.3)
- Recommended dosage in pregnant individuals who are virologically-suppressed (HIV-1 RNA less than 50 copies per mL) on a stable antiretroviral regimen with no known substitutions associated with resistance to the individual components of BIKTARVY: One tablet containing 50 mg BIC, 200 mg FTC, and 25 mg TAF taken orally once daily with or without food. (2.4)
- Renal impairment: BIKTARVY is not recommended in patients with estimated creatinine clearance of 15 to below 30 mL/min, or below 15 mL/min who are not receiving chronic hemodialysis, or below 15 mL/min who have no antiretroviral treatment history. (2.5)
- Hepatic impairment: BIKTARVY is not recommended in patients with severe hepatic impairment. (2.6)

3 DOSAGE FORMS AND STRENGTHS

Tablets: 50 mg of BIC, 200 mg of FTC, and 25 mg of TAF. (3)

Tablets: 30 mg of BIC, 120 mg of FTC, and 15 mg of TAF. (3)

4 CONTRAINDICATIONS

BIKTARVY is contraindicated to be co-administered with:

- dofetilide. (4)
- rifampin. (4)

5 WARNINGS AND PRECAUTIONS

- Immune reconstitution syndrome: May necessitate further evaluation and treatment. (5.3)
- New onset or worsening renal impairment: Assess serum creatinine, estimated creatinine clearance, urine glucose and urine protein when initiating BIKTARVY and during therapy as clinically appropriate in all patients. Also assess serum phosphorus in patients with chronic kidney disease. (5.4)
- Lactic acidosis/severe hepatomegaly with steatosis: Discontinue treatment in patients who develop symptoms or laboratory findings suggestive of lactic acidosis or pronounced hepatotoxicity. (5.5)

6 ADVERSE REACTIONS

Most common adverse reactions (incidence greater than or equal to 5%, all grades) are diarrhea, nausea, and headache. (6.1)

To report SUSPECTED ADVERSE REACTIONS, contact Gilead Sciences, Inc. at 1-800-GILEAD-5 or FDA at 1-800-FDA-1088 or www.fda.gov/medwatch.

7 DRUG INTERACTIONS

- Because BIKTARVY is a complete regimen, coadministration with other antiretroviral medications for the treatment of HIV-1 infection is not recommended. (7.1)
- Consult the Full Prescribing Information prior to and during treatment for important drug interactions. (4, 5.2, 7, 12.3)

8 USE IN SPECIFIC POPULATIONS

- Pediatrics: Not recommended for patients weighing less than 14 kg. (8.4)

FULL PRESCRIBING INFORMATION

WARNING: POST TREATMENT ACUTE EXACERBATION OF HEPATITIS B

Severe acute exacerbations of hepatitis B have been reported in patients with HIV-1 and HBV who have discontinued products containing emtricitabine (FTC) and/or tenofovir disoproxil fumarate (TDF), and may occur with discontinuation of BIKTARVY.

Closely monitor hepatic function with both clinical and laboratory follow-up for at least several months in patients with HIV-1 and HBV who discontinue BIKTARVY. If appropriate, anti-hepatitis B therapy may be warranted [see Warnings and Precautions (5.1)].

1 INDICATIONS AND USAGE

BIKTARVY is indicated as a complete regimen for the treatment of human immunodeficiency virus type 1 (HIV-1) infection in adults and pediatric patients weighing at least 14 kg:

- with no antiretroviral treatment history, or
- with an antiretroviral treatment history and not virologically suppressed, with no known or suspected substitutions associated with resistance to the integrase strand inhibitor class, emtricitabine, or tenofovir, or
- to replace the current antiretroviral regimen in those who are virologically-suppressed (HIV-1 RNA less than 50 copies per mL) on a stable antiretroviral regimen with no known or suspected substitutions associated with resistance to bictegravir or tenofovir [see Dosage and Administration (2.4), and Use in Specific Populations (8.1)].

2 DOSAGE AND ADMINISTRATION

2.1 Testing When Initiating and During Treatment with BIKTARVY

Prior to or when initiating BIKTARVY, test patients for hepatitis B virus infection [see Warnings and Precautions (5.1)].

Prior to or when initiating BIKTARVY, and during treatment with BIKTARVY, assess serum creatinine, estimated creatinine clearance, urine glucose and urine protein in all patients as clinically appropriate. In patients with chronic kidney disease, also assess serum phosphorus [see Warnings and Precautions (5.4)].

2.2 Recommended Dosage in Adults and Pediatric Patients Weighing at Least 25 kg

BIKTARVY is a three-drug fixed dose combination product containing bictegravir (BIC), emtricitabine (FTC), and tenofovir alafenamide (TAF). The recommended dosage of BIKTARVY is one tablet containing 50 mg of BIC, 200 mg of FTC, and 25 mg of TAF taken orally once daily with or without food in [see Dosage and Administration (2.4)]:

- adults and pediatric patients weighing at least 25 kg with an estimated creatinine clearance greater than or equal to 30 mL/min; or
- virologically-suppressed adults with an estimated creatinine clearance below 15 mL/min who are receiving chronic hemodialysis. On days of hemodialysis, administer the daily dose of BIKTARVY after completion of hemodialysis treatment [see Use in Specific Populations (8.4, 8.6), and Clinical Pharmacology (12.3)].

2.3 Recommended Dosage in Pediatric Patients Weighing at Least 14 kg to Less than 25 kg

The recommended dosage of BIKTARVY is one tablet containing 30 mg of BIC, 120 mg of FTC, and 15 mg of TAF taken orally once daily with or without food in:

- pediatric patients weighing at least 14 kg to less than 25 kg with an estimated creatinine clearance greater than or equal to 30 mL/min [see Use in Specific Populations (8.4, 8.6), and Clinical Pharmacology (12.3)].

For children unable to swallow a whole tablet, the tablet can be split and each part taken separately as long as all parts are ingested within approximately 10 minutes.

2.4 Recommended Dosage in Pregnant Individuals

The recommended dosage of BIKTARVY in pregnant individuals is one tablet containing 50 mg of BIC, 200 mg of FTC, and 25 mg of TAF taken orally once daily with or without food in pregnant individuals who are virologically-suppressed (HIV-1 RNA less than 50 copies per mL) on a stable antiretroviral regimen with no known substitutions associated with resistance to any of the individual components of BIKTARVY. Lower exposures of BIKTARVY were observed during pregnancy; therefore, viral load should be monitored closely [see Drug Interactions (7.5), Use in Specific Populations (8.1), and Clinical Pharmacology (12.3)].

2.5 Not Recommended in Patients with Severe Renal Impairment

BIKTARVY is not recommended in patients with [see Dosage and Administration (2.2, 2.3), and Use in Specific Populations (8.6)]:

- severe renal impairment (estimated creatinine clearance of 15 to below 30 mL/min); or
- end stage renal disease (ESRD; estimated creatinine clearance below 15 mL/min who are not receiving chronic hemodialysis; or
- no antiretroviral treatment history and ESRD who are receiving chronic hemodialysis.

2.6 Not Recommended in Patients with Severe Hepatic Impairment

BIKTARVY is not recommended in patients with severe hepatic impairment (Child-Pugh Class C) [see Use in Specific Populations (8.7), and Clinical Pharmacology (12.3)].

3 DOSAGE FORMS AND STRENGTHS

BIKTARVY tablets are available in two dose strengths:

- 50 mg/200 mg/25 mg tablets: 50 mg of bictegravir (BIC) (equivalent to 52.5 mg of bictegravir sodium), 200 mg of emtricitabine (FTC), and 25 mg of tenofovir alafenamide (TAF) (equivalent to 28 mg of tenofovir alafenamide fumarate). These tablets are purplish brown, capsule-shaped, film-coated, and debossed with “GSI” on one side and “9883” on the other side.
- 30 mg/120 mg/15 mg tablets: 30 mg of BIC (equivalent to 31.5 mg of bictegravir sodium), 120 mg of FTC, and 15 mg of TAF (equivalent to 16.8 mg of tenofovir alafenamide fumarate). These tablets are pink, capsule-shaped, film-coated, and either debossed with “GSI” on one side and “B” on the other side; or with a non-functional bisecting score line on one side and “BVY” on the other side.

4 CONTRAINDICATIONS

BIKTARVY is contraindicated to be co-administered with:

- dofetilide due to the potential for increased dofetilide plasma concentrations and associated serious and/or life-threatening events [see Drug Interactions (7.5)].
- rifampin due to decreased BIC plasma concentrations, which may result in the loss of therapeutic effect and development of resistance to BIKTARVY [see Drug Interactions (7.5)].

5 WARNINGS AND PRECAUTIONS

5.1 Severe Acute Exacerbation of Hepatitis B in Patients with HIV-1 and HBV

Patients with HIV-1 should be tested for the presence of chronic hepatitis B virus (HBV) before or when initiating antiretroviral therapy [see Dosage and Administration (2.1)].

Severe acute exacerbations of hepatitis B (e.g., liver decompensation and liver failure) have been reported in patients with HIV-1 and HBV who have discontinued products containing FTC and/or tenofovir disoproxil fumarate (TDF), and may occur with discontinuation of BIKTARVY. Patients with HIV-1 and HBV who discontinue BIKTARVY should be closely monitored with both clinical and laboratory follow-up for at least several months after stopping treatment. If appropriate, anti-hepatitis B therapy may be warranted, especially in patients with advanced liver disease or cirrhosis, since post-treatment exacerbation of hepatitis may lead to hepatic decompensation and liver failure.

5.2 Risk of Adverse Reactions or Loss of Virologic Response Due to Drug Interactions

The concomitant use of BIKTARVY with certain other drugs may result in known or potentially significant drug interactions, some of which may lead to [see Contraindications (4), and Drug Interactions (7.5)]:

- Loss of therapeutic effect of BIKTARVY and possible development of resistance.
- Possible clinically significant adverse reactions from greater exposures of concomitant drugs.

See Table 3 for steps to prevent or manage these possible and known significant drug interactions, including dosing recommendations. Consider the potential for drug interactions prior to and during BIKTARVY therapy; review concomitant medications during BIKTARVY therapy; and monitor for the adverse reactions associated with the concomitant drugs.

5.3 Immune Reconstitution Syndrome

Immune reconstitution syndrome has been reported in patients treated with combination antiretroviral therapy. During the initial phase of combination antiretroviral treatment, patients whose immune system responds may develop an inflammatory response to indolent or residual opportunistic infections [such as Mycobacterium avium infection, cytomegalovirus, Pneumocystis jirovecii pneumonia (PCP), or tuberculosis], which may necessitate further evaluation and treatment.

Autoimmune disorders (such as Graves’ disease, polymyositis, Guillain-Barré syndrome, and autoimmune hepatitis) have also been reported to occur in the setting of immune reconstitution; however, the time to onset is more variable, and can occur many months after initiation of treatment.

5.4 New Onset or Worsening Renal Impairment

Postmarketing cases of renal impairment, including acute renal failure, proximal renal tubulopathy (PRT), and Fanconi syndrome, have been reported with TAF-containing products; while most of these cases were characterized by potential confounders that may have contributed to the reported renal events, it is also possible these factors may have predisposed patients to tenofovir-related adverse events [see Adverse Reactions (6.1, 6.2)]. BIKTARVY is not recommended in patients with severe renal impairment (estimated creatinine clearance of 15 to below 30 mL/min), or patients with ESRD (estimated creatinine clearance below 15 mL/min) who are not receiving chronic hemodialysis, or patients with no antiretroviral treatment history and ESRD who are receiving chronic hemodialysis [see Dosage and Administration (2.4), and Use in Specific Populations (8.6)].

Patients taking tenofovir prodrugs who have impaired renal function and those taking nephrotoxic agents including non-steroidal anti-inflammatory drugs are at increased risk of developing renal-related adverse reactions.

Prior to or when initiating BIKTARVY, and during treatment with BIKTARVY, assess serum creatinine, estimated creatinine clearance, urine glucose and urine protein in all patients as clinically appropriate. In patients with chronic kidney disease, also assess serum phosphorus. Discontinue BIKTARVY in patients who develop clinically significant decreases in renal function or evidence of Fanconi syndrome.

5.5 Lactic Acidosis/Severe Hepatomegaly with Steatosis

Lactic acidosis and severe hepatomegaly with steatosis, including fatal cases, have been reported with the use of nucleoside analogs, including emtricitabine, a component of BIKTARVY, and tenofovir DF, another prodrug of tenofovir, alone or in combination with other antiretrovirals. Treatment with BIKTARVY should be suspended in any patient who develops clinical or laboratory findings suggestive of lactic acidosis or pronounced hepatotoxicity (which may include hepatomegaly and steatosis even in the absence of marked transaminase elevations).

6 ADVERSE REACTIONS

The following adverse reactions are discussed in other sections of the labeling:

- Severe Acute Exacerbations of Hepatitis B [see Warnings and Precautions (5.1)].
- Immune Reconstitution Syndrome [see Warnings and Precautions (5.3)].
- New Onset or Worsening Renal Impairment [see Warnings and Precautions (5.4)].
- Lactic Acidosis/Severe Hepatomegaly with Steatosis [see Warnings and Precautions (5.5)].

6.1 Clinical Trials Experience

Because clinical trials are conducted under widely varying conditions, adverse reaction rates observed in the clinical trials of a drug cannot be directly compared to rates in the clinical trials of another drug and may not reflect the rates observed in practice.

Clinical Trials in Adults with No Antiretroviral Treatment History

The primary safety assessment of BIKTARVY was based on data from two randomized, double-blind, active-controlled trials, Trial 1489 and Trial 1490, that enrolled 1274 adult participants with HIV-1 and no antiretroviral treatment history through Week 144. After Week 144, participants received open-label BIKTARVY in an optional extension phase for an additional 96 weeks (end of study). A total of 634 and 1025 participants received one tablet of BIKTARVY once daily during the double-blind (Week 144) and extension phases, respectively [see Clinical Studies (14.2)].

The most common adverse reactions (all Grades) reported in at least 5% of participants in the BIKTARVY group in either Trial 1489 or Trial 1490 were diarrhea, nausea, and headache. The proportion of participants who discontinued treatment through Week 144 with BIKTARVY, abacavir [ABC]/dolutegravir [DTG]/ lamivudine [3TC]), or DTG + FTC/TAF, due to adverse events, regardless of severity, was 1%, 2%, and 2%, respectively. Table 1 displays the frequency of adverse reactions (all Grades) greater than or equal to 2% in the BIKTARVY group.

Table 1 Adverse Reactions [Frequencies of adverse reactions are based on all adverse events attributed to trial drugs by the investigator. No adverse reactions of Grade 2 or higher occurred in > 1% of participants treated with BIKTARVY.] (All Grades) Reported in ≥ 2% of Adults with HIV-1 and No Antiretroviral Treatment History Receiving BIKTARVY in Trials 1489 or 1490 (Week 144 analysis)
 | Trial 1489 |  | Trial 1490
Adverse Reactions | BIKTARVY N=314 | ABC/DTG/3TC N=315 | BIKTARVY N=320 | DTG + FTC/TAF N=325
Diarrhea | 6% | 4% | 3% | 3%
Nausea | 6% | 18% | 3% | 5%
Headache | 5% | 5% | 4% | 3%
Fatigue | 3% | 4% | 2% | 2%
Abnormal dreams | 3% | 3% | <1% | 1%
Dizziness | 2% | 3% | 2% | 1%
Insomnia | 2% | 3% | 2% | <1%
Abdominal distention | 2% | 2% | 1% | 2%

Additional adverse reactions (all Grades) occurring in less than 2% of participants administered BIKTARVY in Trials 1489 and 1490 included vomiting, flatulence, dyspepsia, abdominal pain, rash, and depression.

Suicidal ideation, suicide attempt, and depression suicidal occurred in 2% of participants administered BIKTARVY; these events occurred primarily in participants with a preexisting history of depression, prior suicide attempt or psychiatric illness.

The majority (84%) of adverse events associated with BIKTARVY were Grade 1.

Adverse reactions in the open-label extension phases of Trials 1489 and 1490 were similar to those observed in participants administered BIKTARVY in the Week 144 analysis.

Clinical Trials in Adults with Virologically-Suppressed HIV-1

The safety of BIKTARVY in virologically-suppressed adults was based on Week 48 data from 282 participants in a randomized, double-blind, active-controlled trial (Trial 1844) in which virologically-suppressed participants were switched from either DTG + ABC/3TC or ABC/DTG/3TC to BIKTARVY; Week 48 data from 290 participants in an open-label, active-controlled trial in which virologically-suppressed participants were switched from a regimen containing atazanavir (ATV) (given with cobicistat or ritonavir) or darunavir (DRV) (given with cobicistat or ritonavir) plus either FTC/TDF or ABC/3TC, to BIKTARVY (Trial 1878); and Week 48 data from a randomized, double-blind active-controlled trial in which 284 virologically-suppressed participants were switched from DTG plus either FTC/TAF or FTC/TDF, to BIKTARVY (Trial 4030). Overall, the safety profile in virologically-suppressed adult participants in Trials 1844, 1878, and 4030 was similar to that in participants with no antiretroviral treatment history [see Clinical Studies (14.3)].

Clinical Trial in Adults with End Stage Renal Disease (ESRD) Receiving Chronic Hemodialysis

The safety of FTC and TAF (components of BIKTARVY) was evaluated in a single arm, open-label trial (Trial 1825) in virologically-suppressed adults with ESRD (estimated creatinine clearance of less than 15 mL/min) on chronic hemodialysis treated with FTC+TAF in combination with elvitegravir and cobicistat as a fixed-dose combination tablet for 96 weeks (N=55). The most commonly reported adverse reaction (adverse event assessed as causally related by investigator and all grades) was nausea (7%). Serious adverse events were reported in 65% of participants and the most common serious adverse events were pneumonia (15%), fluid overload (7%), hyperkalemia (11%) and osteomyelitis (7%). Overall 7% of participants permanently discontinued treatment due to an adverse event. In an extension phase of Trial 1825 in which 10 participants switched to BIKTARVY for 48 weeks, the safety findings were similar to those in the initial phase of the open-label trial [see Use in Specific Populations (8.6), and Clinical Studies (14.3)].

Laboratory Abnormalities

The frequency of laboratory abnormalities (Grades 3–4) occurring in at least 2% of participants receiving BIKTARVY in Trials 1489 and 1490 are presented in Table 2.

Table 2 Laboratory Abnormalities (Grades 3–4) Reported in ≥ 2% of Participants Receiving BIKTARVY in Trials 1489 or 1490 (Week 144 analysis)
 | Trial 1489 |  | Trial 1490
Laboratory Parameter Abnormality [Frequencies are based on treatment-emergent laboratory abnormalities.] | BIKTARVY N=314 | ABC/DTG/3TC N=315 | BIKTARVY N=320 | DTG + FTC/TAF N=325
Amylase (>2.0 × ULN) | 3% | 4% | 3% | 4%
ALT (>5.0 × ULN) | 2% | 2% | 3% | 1%
AST (>5.0 × ULN) | 5% | 3% | 2% | 3%
Creatine Kinase (≥10.0 × ULN) | 8% | 8% | 6% | 4%
Neutrophils (<750 mm^3) | 3% | 4% | 3% | 2%
LDL-cholesterol (fasted) (>190 mg/dL) | 5% | 5% | 4% | 6%
Lipase (> 3.0 × ULN) [Lipase test performed only in participants with serum amylase > 1.5 × ULN.] | 2% | 2% | <1% | 2%
GGT (>5.0 × ULN) | 2% | 2% | 1% | 1%
ULN = Upper limit of normal

Changes in Serum Creatinine: BIC has been shown to increase serum creatinine due to inhibition of tubular secretion of creatinine without affecting renal glomerular function [see Clinical Pharmacology (12.2)]. Increases in serum creatinine occurred by Week 4 of treatment and remained stable through Week 144. In Trials 1489 and 1490, median (Q1, Q3) serum creatinine increased by 0.11 (0.03, 0.19) mg per dL from baseline to Week 144 in the BIKTARVY group and was similar to the comparator groups who received ABC/DTG/3TC, or DTG + FTC/TAF. There were no discontinuations due to renal adverse events and renal serious adverse events were encountered in less than 1% of participants treated with BIKTARVY through Week 144 in clinical trials.

Changes in Bilirubin: In Trials 1489 and 1490, total bilirubin increases were observed in 17% of participants administered BIKTARVY through Week 144. Increases were primarily Grade 1 (1.0 to 1.5 × ULN) (12%) and Grade 2 (1.5 to 2.5 x ULN) (4%). Graded bilirubin increases in the ABC/DTG/3TC, and DTG + FTC/TAF groups, were 7% and 8%, respectively. Increases were primarily Grade 1 (5% ABC/DTG/3TC and 7% DTG + FTC/TAF) or Grade 2 (2% ABC/DTG/3TC and 2% DTG + FTC/TAF). There were no discontinuations due to hepatic adverse events through Week 144 in BIKTARVY clinical studies.

Clinical Trials in Pediatric Participants

The safety of BIKTARVY was evaluated in participants with virologically-suppressed HIV-1 between the ages of 12 to less than 18 years and weighing at least 35 kg (N=50) through Week 48 (cohort 1), in virologically-suppressed participants between the ages of 6 to less than 12 years and weighing at least 25 kg (N=50) through Week 24 (cohort 2), and in virologically suppressed participants at least 2 years of age and weighing at least 14 to less than 25 kg (N=22) through Week 24 (cohort 3) in an open label clinical trial (Trial 1474) [see Clinical Studies (14.4)]. No new adverse reactions or laboratory abnormalities were identified compared to those observed in adults. Adverse reactions were reported in 11% of pediatric participants. The majority (76%) of adverse reactions were Grade 1. No Grade 3 or 4 adverse reactions were reported. The adverse reaction reported by more than one subject (regardless of severity) was abdominal discomfort (n=2). One subject (1%) had Grade 2 adverse reactions of insomnia and anxiety that led to discontinuation of BIKTARVY. The other adverse reactions that occurred in single participants were similar to those seen in adults.

6.2 Postmarketing Experience

The following events have been identified during post approval use of BIKTARVY or products containing TAF. Because these events are reported voluntarily from a population of uncertain size, it is not always possible to reliably estimate their frequency or establish a causal relationship to drug exposure.

Renal and Urinary Disorders

Acute renal failure, acute tubular necrosis, proximal renal tubulopathy, and Fanconi syndrome

Skin and Subcutaneous Tissue Disorders

Angioedema, Stevens-Johnson syndrome/toxic epidermal necrolysis, and urticaria

Investigations

Weight increased

7 DRUG INTERACTIONS

7.1 Other Antiretroviral Medications

Because BIKTARVY is a complete regimen, coadministration with other antiretroviral medications for the treatment of HIV-1 infection is not recommended [see Indications and Usage (1)]. Comprehensive information regarding potential drug-drug interactions with other antiretroviral medications is not provided because the safety and efficacy of concomitant HIV-1 antiretroviral therapy is unknown.

7.2 Potential for BIKTARVY to Affect Other Drugs

BIC inhibits organic cation transporter 2 (OCT2) and multidrug and toxin extrusion transporter 1 (MATE1) in vitro. Coadministration of BIKTARVY with drugs that are substrates of OCT2 and MATE1 (e.g., dofetilide) may increase their plasma concentrations (see Table 3).

7.3 Potential Effect of Other Drugs on One or More Components of BIKTARVY

BIC is a substrate of CYP3A and UGT1A1. A drug that is a strong inducer of CYP3A and also an inducer of UGT1A1 can substantially decrease the plasma concentrations of BIC which may lead to loss of therapeutic effect of BIKTARVY and development of resistance [see Clinical Pharmacology (12.3)].

The use of BIKTARVY with a drug that is a strong inhibitor of CYP3A and also an inhibitor of UGT1A1 may significantly increase the plasma concentrations of BIC.

TAF is a substrate of P-glycoprotein (P-gp) and breast cancer resistance protein (BCRP). Co-administration of drugs that inhibit P-gp and BCRP may increase the absorption and plasma concentrations of TAF [see Clinical Pharmacology (12.3)]. Co-administration of drugs that induce P-gp activity are expected to decrease the absorption of TAF, resulting in decreased plasma concentration of TAF, which may lead to loss of therapeutic effect of BIKTARVY and development of resistance (see Table 3).

7.4 Drugs Affecting Renal Function

Because FTC and tenofovir are primarily excreted by the kidneys by a combination of glomerular filtration and active tubular secretion, coadministration of BIKTARVY with drugs that reduce renal function or compete for active tubular secretion may increase concentrations of FTC, tenofovir, and other renally eliminated drugs and this may increase the risk of adverse reactions. Some examples of drugs that are eliminated by active tubular secretion include, but are not limited to, acyclovir, cidofovir, ganciclovir, valacyclovir, valganciclovir, aminoglycosides (e.g., gentamicin), and high-dose or multiple NSAIDs [see Warnings and Precautions (5.4)].

7.5 Established and Potentially Significant Drug Interactions

Table 3 provides a listing of established or potentially clinically significant drug interactions with recommended prevention or management strategies. The drug interactions described are based on studies conducted with either BIKTARVY, the components of BIKTARVY (BIC, FTC, and TAF) as individual agents, or are drug interactions that may occur with BIKTARVY [see Contraindications (4), Warnings and Precautions (5.2), and Clinical Pharmacology (12.3)].

Table 3 Established and Potentially Significant [Table is not all inclusive.] Drug Interactions: Alteration in Regimen May be Recommended
Concomitant Drug Class: Drug Name | Effect on Concentration [↑ = Increase, ↓ = Decrease.] | Clinical Comment
Antiarrhythmics: dofetilide | ↑ Dofetilide | Coadministration is contraindicated due to the potential for serious and/or life-threatening events associated with dofetilide therapy [see Contraindications (4)].
Anticonvulsants: carbamazepine [Drug-drug interaction study was conducted with either BIKTARVY or its components as individual agents.] oxcarbazepine phenobarbital phenytoin | ↓ BIC ↓ TAF | Coadministration with alternative anticonvulsants should be considered.
Antimycobacterials: rifabutin rifampin, [Strong inducer of CYP3Aand P-gp, and inducer of UGT1A1.] rifapentine | ↓ BIC ↓ TAF | Coadministration with rifampin is contraindicated due to the effect of rifampin on the BIC component of BIKTARVY [see Contraindications (4)]. Coadministration with rifabutin or rifapentine is not recommended.
Herbal Products: St. John’s wort [The induction potency of St. John’s wort may vary widely based on preparation.] | ↓ BIC ↓ TAF | Coadministration with St. John’s wort is not recommended.
Oral medications or supplements containing polyvalent cations (e.g., Mg, Al, Ca, Fe): Calcium or iron supplements Cation-containing antacids or laxatives Sucralfate Buffered medications | ↓ BIC | Antacids containing Al/Mg: BIKTARVY can be taken at least 2 hours before or 6 hours after taking antacids containing Al/Mg. Routine administration of BIKTARVY together with, or 2 hours after, antacids containing Al/Mg is not recommended. Supplements or Antacids containing Calcium or Iron: BIKTARVY and supplements or antacids containing calcium or iron can be taken together with food. Routine administration of BIKTARVY under fasting conditions together with, or 2 hours after, supplements or antacids containing calcium or iron is not recommended. In pregnant individuals: Antacids containing Al/Mg: BIKTARVY can be taken at least 2 hours before or 6 hours after antacids containing Al/Mg regardless of food intake. Supplements or Antacids containing Calcium or Iron: BIKTARVY and supplements or antacids containing calcium or iron can be taken together with food; but when taken on an empty stomach, BIKTARVY should be taken at least 2 hours before or 6 hours after supplements or antacids containing calcium or iron.
Metformin | ↑ Metformin | Refer to the prescribing information of metformin for assessing the benefit and risk of concomitant use of BIKTARVY and metformin.

7.6 Drugs without Clinically Significant Interactions with BIKTARVY

Based on drug interaction studies conducted with BIKTARVY or the components of BIKTARVY, no clinically significant drug interactions have been observed when BIKTARVY is combined with the following drugs: ethinyl estradiol, ledipasvir/sofosbuvir, midazolam, norgestimate, sertraline, sofosbuvir, sofosbuvir/velpatasvir, and sofosbuvir/velpatasvir/voxilaprevir.

8 USE IN SPECIFIC POPULATIONS

8.1 Pregnancy

Pregnancy Exposure Registry

There is a pregnancy exposure registry that monitors pregnancy outcomes in individuals exposed to BIKTARVY during pregnancy. Healthcare providers are encouraged to register patients by calling the Antiretroviral Pregnancy Registry (APR) at 1-800-258-4263.

Risk Summary

Available data from observational studies and the APR with BIC, FTC and TAF use during pregnancy have not established a drug-associated risk of major birth defects, miscarriage or other adverse maternal or fetal outcomes. Reports of pregnant individuals treated with products containing BIC, FTC, or TAF contribute to APR’s overall risk assessment for these components. Available data from the APR show no statistically significant difference in the overall risk of major birth defects for BIC, FTC, or TAF compared with the background rate for major birth defects of 2.7% in a U.S. reference population of the Metropolitan Atlanta Congenital Defects Program (MACDP) (see Data). The rate of miscarriage is not reported in the APR. The estimated background rate of miscarriage in the clinically recognized pregnancies in the U.S. general population is 15-20%.

BIKTARVY safety has also been evaluated in an open-label trial that demonstrated safety findings that were consistent with other trials in adults (see Data).

In animal reproduction studies, no evidence of adverse developmental outcomes was observed with the components of BIKTARVY at exposures that were either not maternally toxic (rabbits) or greater than (rats and mice) those in humans at the recommended human dose (RHD) (see Data). During organogenesis, systemic exposures (AUC) to BIC were approximately 36 (rats) and 0.6 times (rabbits), to FTC were approximately 60 (mice) and 108 times (rabbits), and to TAF were approximately 2 (rats) and 78 times (rabbits) the exposure at the RHD of BIKTARVY. In rat pre/postnatal development studies, maternal systemic exposures (AUC) were 30 times (BIC), 60 times (FTC), and 19 times (TDF) the exposures of each component in humans at the RHD.

Data

Human Data

BIKTARVY was evaluated in an open-label clinical trial of 33 virologically-suppressed (HIV-1 RNA < 50 copies/mL) pregnant adults with HIV-1 and no known substitutions associated with resistance to BIC, FTC, or TAF. Pregnant adults were administered BIKTARVY (containing 50 mg of BIC, 200 mg of FTC and 25 mg of TAF) once daily from the second or third trimester through postpartum. Exposures of BIC, FTC, and TAF were lower during pregnancy as compared to postpartum [see Clinical Pharmacology (12.3)]. All 32 adult participants who completed the study maintained viral suppression during pregnancy, at delivery, and through Week 18 postpartum. The median CD4+ cell count at baseline was 558 cells/µL, and the median change in CD4+ cell count from baseline to Week 12 postpartum was 159 cells/μL. All 29 neonate participants had negative/nondetectable HIV-1 PCR results at birth and/or at 4 to 8 weeks post-birth. The safety findings in this trial were consistent with other trials in adults.

BIKTARVY was only studied in pregnant individuals who were virologically-suppressed, and lower plasma exposures of BIKTARVY were observed during pregnancy compared to post-partum. Therefore, BIKTARVY is recommended in pregnant individuals who are virologically-suppressed on a stable antiretroviral regimen with no known substitutions associated with resistance to any of the individual components of BIKTARVY.

Bictegravir (BIC):

Based on prospective reports to the APR of over 500 exposures to a BIC-containing regimen during pregnancy resulting in live births (including 423 exposed in the first trimester and 113 exposed in the second/third trimester), the prevalence of birth defects in live births was 4.3% (95% CI: 2.5% to 6.6%) and 1.8% (0.2%, 6.2%) following first and second/third trimester exposure, respectively, to a BIC-containing regimen.

Emtricitabine (FTC):

Based on prospective reports to the APR of over 6,500 exposures to FTC-containing regimens during pregnancy resulting in live births (including over 4,800 exposed in the first trimester and over 1,700 exposed in the second/third trimester), the prevalence of birth defects in live births was 2.9% (95% CI: 2.5% to 3.4%) and 2.8% (95% CI: 2.1% to 3.7%) following first and second/third trimester exposure, respectively, to FTC-containing regimens.

Tenofovir Alafenamide (TAF):

Based on prospective reports to the APR of over 1,200 exposures to TAF-containing regimens during pregnancy resulting in live births (including over 1000 exposed in the first trimester and over 200 exposed in the second/third trimester), the prevalence of birth defects in live births was 3.9% (95% CI: 2.8% to 5.2%) and 4.8% (95% CI: 2.5% to 8.3%) following first and second/third trimester exposure, respectively, to TAF-containing regimens.

Methodological limitations of the APR include the use of MACDP as the external comparator group. The MACDP population is not disease-specific, evaluates individuals and infants from a limited geographic area, and does not include outcomes for births that occurred at less than 20 weeks gestation.

Animal Data

Bictegravir: BIC was administered orally to pregnant rats (5, 30, or 300 mg/kg/day) and rabbits (100, 300, or 1000 mg/kg/day) on gestation days 7 through 17, and 7 through 19, respectively. No adverse embryo-fetal effects were observed in rats and rabbits at BIC exposures (AUC) of up to approximately 36 (rats) and 0.6 (rabbits) times the exposure in humans at the RHD of BIKTARVY. Spontaneous abortion, increased clinical signs [fecal changes, thin body, and cold-to-touch], and decreased body weight were observed at a maternally toxic dose in rabbits (1000 mg/kg/day; approximately 1.4 times higher than human exposure at the RHD).

In a pre/postnatal development study, BIC was administered orally to pregnant rats (up to 300 mg/kg/day) from gestation days 6 to lactation/post-partum day 24. No significant adverse effects were observed in the offspring exposed daily from before birth (in utero) through lactation at maternal and pup exposures (AUC) of approximately 30 and 11 times higher, respectively, than human exposures at the RHD.

Emtricitabine: FTC was administered orally to pregnant mice (250, 500, or 1000 mg/kg/day) and rabbits (100, 300, or 1000 mg/kg/day) through organogenesis (on gestation days 6 through 15, and 7 through 19, respectively). No significant toxicological effects were observed in embryo-fetal toxicity studies performed with emtricitabine in mice at exposures approximately 60 times higher and in rabbits at approximately 108 times higher than human exposures at the RHD.

In a pre/postnatal development study with FTC, mice were administered doses up to 1000 mg/kg/day; no significant adverse effects directly related to drug were observed in the offspring exposed daily from before birth (in utero) through sexual maturity at daily exposures (AUC) of approximately 60 times higher than human exposures at the RHD.

Tenofovir alafenamide: TAF was administered orally to pregnant rats (25, 100, or 250 mg/kg/day) and rabbits (10, 30, or 100 mg/kg/day) through organogenesis (on gestation days 6 through 17, and 7 through 20, respectively). No adverse embryo-fetal effects were observed in rats and rabbits at TAF exposures of approximately 2 (rats) and 78 (rabbits) times higher than the exposure in humans at the recommended daily dose of BIKTARVY. TAF is rapidly converted to tenofovir; the observed tenofovir exposure in rats and rabbits were 55 (rats) and 86 (rabbits) times higher than human tenofovir exposures at the RHD. Since TAF is rapidly converted to tenofovir and lower tenofovir exposures in rats and mice were observed after TAF administration compared to TDF administration, a pre/postnatal development study in rats was conducted only with TDF. Doses up to 600 mg/kg/day were administered through lactation; no adverse effects were observed in the offspring on gestation day 7 [and lactation day 20] at tenofovir exposures of approximately 12 [19] times higher than the exposures in humans at the RHD of BIKTARVY.

8.2 Lactation

Risk Summary

Data from the published literature report the presence of BIC, FTC, TAF, and tenofovir in human milk. There are no data on the effects of BIC on the breastfed child. Data from the published literature have not reported adverse effects of FTC or TAF on a breastfed child. There are no data on the effects of BIC, FTC or TAF on milk production.

Potential risks of breastfeeding include: (1) HIV-1 transmission to HIV-1–negative infants; (2) developing viral resistance in HIV-1–positive infants; and (3) adverse reactions in a breastfed infant similar to those seen in adults.

8.4 Pediatric Use

The safety and effectiveness of BIKTARVY have been established as a complete regimen for the treatment of human immunodeficiency virus type 1 (HIV-1) infection in pediatric patients weighing at least 14 kg:

- who have no antiretroviral treatment history, or
- with an antiretroviral treatment history and not virologically suppressed, with no known or suspected substitutions associated with resistance to the integrase strand inhibitor class, emtricitabine, or tenofovir, or
- to replace the current antiretroviral regimen in those who are virologically-suppressed (HIV-1 RNA less than 50 copies per mL) on a stable antiretroviral regimen with no known or suspected resistance to bictegravir or tenofovir [see Indications and Usage (1), and Dosage and Administration (2.2, 2.3)].

Use of BIKTARVY in pediatric patients weighing at least 14 kg is supported by the following:

- trials in adults [see Clinical Studies (14.1, 14.3)]
- an open-label trial in three age-based cohorts of virologically-suppressed pediatric participants [see Clinical Studies (14.4)]
  - Cohort 1: 12 to less than 18 years of age and weighing at least 35 kg receiving BIKTARVY through Week 48 (N=50),
  - Cohort 2: 6 to less than 12 years of age and weighing at least 25 kg receiving BIKTARVY through Week 24 (N=50), and
  - Cohort 3: at least 2 years of age and weighing at least 14 to less than 25 kg through Week 24 (N=22). No pediatric participants 2 years of age were enrolled; of the 6 pediatric participants who were 3 years of age at enrollment, 3 participants weighed between 14 to less than 15 kg.

The safety and efficacy of BIKTARVY in these pediatric participants were similar to that in adults, and there was no clinically significant change in exposure for the components of BIKTARVY [see Adverse Reactions (6.1), Clinical Pharmacology (12.3), and Clinical Studies (14.4)].

Safety and effectiveness of BIKTARVY in pediatric patients weighing less than 14 kg have not been established.

8.5 Geriatric Use

Clinical trials in virologically-suppressed participants (Trials 4449, 1844, and 1878) included 111 participants aged 65 years and over who received BIKTARVY, including 86 patients from an open-label, single-arm trial of participants aged 65 years and over who were switched from their previous antiretroviral regimen to BIKTARVY [see Clinical Studies (14.3)]. Of the total number of BIKTARVY-treated patients in these trials, 100 (90%) were 65 to 74 years of age, and 11 (10%) were 75 to 84 years of age. No overall differences in safety or effectiveness were observed between elderly participants and adults between 18 and less than 65 years of age, and other reported clinical experience has not identified differences in responses between the elderly and younger patients, but greater sensitivity of some older individuals cannot be ruled out.

8.6 Renal Impairment

The pharmacokinetics, safety, virologic and immunologic responses of FTC and TAF (components of BIKTARVY) were evaluated in a single arm, open-label trial (Trial 1825) in virologically-suppressed adults with ESRD (estimated creatinine clearance of less than 15 mL/min) on chronic hemodialysis treated with FTC+TAF in combination with elvitegravir and cobicistat as a fixed-dose combination tablet for 96 weeks (N=55). In an extension phase of Trial 1825, 10 virologically-suppressed participants switched to BIKTARVY and all remained virologically suppressed for 48 weeks [see Adverse Reactions (6.1), Clinical Pharmacology (12.3), and Clinical Studies (14.3)].

No dosage adjustment of BIKTARVY is recommended in patients with estimated creatinine clearance greater than or equal to 30 mL/min, or in virologically-suppressed adults (estimated creatinine clearance below 15 mL/min) who are receiving chronic hemodialysis. On days of hemodialysis, administer the daily dose of BIKTARVY after completion of hemodialysis treatment [see Dosage and Administration (2.2)]

BIKTARVY is not recommended in patients with estimated creatinine clearance of below 30 mL/min, by Cockcroft-Gault, or patients with ESRD (estimated creatinine clearance below 15 mL/min) who are not receiving chronic dialysis, or patients with no antiretroviral treatment history and ESRD who are receiving chronic dialysis, as the safety and/or efficacy of BIKTARVY has not been established in these populations [see Dosage and Administration (2.4), Warnings and Precautions (5.4), and Clinical Pharmacology (12.3)].

8.7 Hepatic Impairment

No dosage adjustment of BIKTARVY is recommended in patients with mild (Child-Pugh Class A) or moderate (Child-Pugh Class B) hepatic impairment. BIKTARVY has not been studied in patients with severe hepatic impairment (Child-Pugh Class C). Therefore, BIKTARVY is not recommended for use in patients with severe hepatic impairment [see Dosage and Administration (2.4), and Clinical Pharmacology (12.3)].

10 OVERDOSAGE

No data are available on overdose of BIKTARVY in patients. If overdose occurs, monitor the patient for evidence of toxicity. Treatment of overdose with BIKTARVY consists of general supportive measures including monitoring of vital signs as well as observation of the clinical status of the patient.

Hemodialysis treatment removes approximately 30% of the FTC dose over a 3-hour dialysis period starting within 1.5 hours of FTC dosing (blood flow rate of 400 mL/min and a dialysate flow rate of 600 mL/min). It is not known whether FTC can be removed by peritoneal dialysis.

Tenofovir is efficiently removed by hemodialysis with an extraction coefficient of approximately 54%.

11 DESCRIPTION

BIKTARVY (bictegravir, emtricitabine, and tenofovir alafenamide) is a fixed dose combination tablet containing bictegravir (BIC), emtricitabine (FTC), and tenofovir alafenamide (TAF) for oral administration.

- BIC is an integrase strand transfer inhibitor (INSTI).
- FTC, a synthetic nucleoside analog of cytidine, is an HIV nucleoside analog reverse transcriptase inhibitor (HIV NRTI).
- TAF, an HIV NRTI, is converted in vivo to tenofovir, an acyclic nucleoside phosphonate (nucleotide) analog of adenosine 5′-monophosphate.

BIKTARVY tablets are available in two dose strengths:

- 50 mg/200 mg/25 mg tablet containing 50 mg of BIC (equivalent to 52.5 mg of bictegravir sodium), 200 mg of FTC, and 25 mg of TAF (equivalent to 28 mg of tenofovir alafenamide fumarate).
- 30 mg/120 mg/15 mg tablet containing 30 mg of BIC (equivalent to 31.5 mg of bictegravir sodium), 120 mg of FTC, and 15 mg of TAF (equivalent to 16.8 mg of tenofovir alafenamide fumarate).

Both dose strengths of BIKTARVY tablets include the following inactive ingredients: croscarmellose sodium, magnesium stearate, and microcrystalline cellulose. The tablets for both dose strengths are film-coated with a coating material containing iron oxide black, iron oxide red, polyethylene glycol, polyvinyl alcohol, talc, and titanium dioxide.

Bictegravir: The chemical name of bictegravir sodium is 2,5-Methanopyrido[1’,2’:4,5]pyrazino[2,1-b][1,3]oxazepine-10-carboxamide, 2,3,4,5,7,9,13,13a-octahydro-8-hydroxy-7,9-dioxo-N-[(2,4,6-trifluorophenyl)methyl]-, sodium salt (1:1), (2R,5S,13aR)-.

Bictegravir sodium has a molecular formula of C21H17F3N3NaO5 and a molecular weight of 471.4 and has the following structural formula:

Bictegravir sodium is an off-white to yellow solid with a solubility of 0.1 mg per mL in water at 20 °C.

Emtricitabine: The chemical name of FTC is 4-amino-5-fluoro-1-(2R-hydroxymethyl-1,3-oxathiolan-5S-yl)-(1H)-pyrimidin-2-one. FTC is the (-)enantiomer of a thio analog of cytidine, which differs from other cytidine analogs in that it has a fluorine in the 5 position.

FTC has a molecular formula of C8H10FN3O3S and a molecular weight of 247.2 and has the following structural formula:

FTC is a white to off-white powder with a solubility of approximately 112 mg per mL in water at 25 °C.

Tenofovir alafenamide: The chemical name of tenofovir alafenamide fumarate drug substance is L-alanine, N-[(S)-[[(1R)-2-(6-amino-9H-purin-9-yl)-1-methylethoxy]methyl]phenoxyphosphinyl]-, 1-methylethyl ester, (2E)-2-butenedioate (2:1).

Tenofovir alafenamide fumarate has an empirical formula of C21H29O5N6P•½(C4H4O4) and a formula weight of 534.5 and has the following structural formula:

Tenofovir alafenamide fumarate is a white to off-white or tan powder with a solubility of 4.7 mg per mL in water at 20 °C.

12 CLINICAL PHARMACOLOGY

12.1 Mechanism of Action

BIKTARVY is a fixed dose combination of antiretroviral drugs bictegravir (BIC), emtricitabine (FTC), and tenofovir alafenamide (TAF) [see Microbiology (12.4)].

12.2 Pharmacodynamics

Cardiac Electrophysiology

In a thorough QT/QTc trial in 48 healthy participants, BIC at doses 1.5 and 6 times the recommended dose did not affect the QT/QTc interval and did not prolong the PR interval. In a thorough QT/QTc trial in 48 healthy participants, TAF at the recommended dose or at a dose 5 times the recommended dose, did not affect the QT/QTc interval and did not prolong the PR interval. The effect of FTC on the QT interval is not known.

Effects on Serum Creatinine

Mean change from baseline in serum creatinine in healthy participants who received BIC 75 mg (1.5 times the approved recommended dosage) once daily with food for 14 days was 0.1 mg per dL on Days 7 and 14 compared to placebo. BIC did not have a significant effect on the estimated creatinine clearance or on the actual glomerular filtration rate (determined by the clearance of probe drug, iohexol).

12.3 Pharmacokinetics

The pharmacokinetic (PK) properties of BIKTARVY components are provided in Table 4. The multiple dose PK parameters of BIKTARVY components (based on population pharmacokinetic analysis) are provided in Table 5.

Table 4 Pharmacokinetic Properties of the Components of BIKTARVY
 |  | Bictegravir (BIC) | Emtricitabine (FTC) | Tenofovir Alafenamide (TAF)
Absorption
Tmax (h) [Values reflect administration of BIKTARVY with or without food.] |  | 2.0–4.0 | 1.5–2.0 | 0.5–2.0
Effect of high-fat meal (relative to fasting) [Values refer to geometric mean ratio [high-fat meal/ fasting] in PK parameters and (90% confidence interval). High fat meal is approximately 800 kcal, 50% fat.] | AUC ratio | 1.24 (1.16, 1.33) | 0.96 (0.93, 0.99) | 1.63 (1.43, 1.85)
 | Cmax ratio | 1.13 (1.06, 1.20) | 0.86 (0.78, 0.93) | 0.92 (0.73, 1.14)
Distribution
% bound to human plasma proteins |  | >99 | <4 | ~80
Blood-to-plasma ratio |  | 0.64 | 0.6 | 1.0
Elimination
t1/2 (h) [t1/2 values refer to median (Q1, Q3) terminal plasma half-life. Note that the active metabolite of TAF, tenofovir diphosphate, has a half-life of 150-180 hours within PBMCs.] |  | 17.3 (14.8, 20.7) | 10.4 (9.0, 12.0) | 0.51 (0.45, 0.62)
Metabolism
Metabolic pathway(s) |  | CYP3A UGT1A1 | Not significantly metabolized | Cathepsin A [In vivo, TAF is hydrolyzed within cells to form tenofovir (major metabolite), which is phosphorylated to the active metabolite, tenofovir diphosphate. In vitro studies have shown that TAF is metabolized to tenofovir by cathepsin A in PBMCs and macrophages; and by CES1 in hepatocytes.] (PBMCs) CES1 (hepatocytes)
Excretion
Major route of elimination |  | Metabolism | Glomerular filtration and active tubular secretion | Metabolism
% of dose excreted in urine [Dosing in mass balance studies: single dose administration of [^14C] BIC; single dose administration of [^14C] FTC after multiple dosing of FTC for ten days; single dose administration of [^14C] TAF.] |  | 35 | 70 | <1
% of dose excreted in feces |  | 60.3 | 13.7 | 31.7
PBMCs=peripheral blood mononuclear cells; CES1=carboxylesterase 1

Table 5 Multiple Dose PK Parameters of BIC, FTC, and TAF Following Oral Administration of BIKTARVY in HIV-Infected Adults
Parameter Mean (CV%) | Bictegravir | Emtricitabine | Tenofovir Alafenamide
Cmax (microgram per mL) | 6.15 (22.9) | 2.13 (34.7) | 0.121 (15.4)
AUCtau (microgram•h per mL) | 102 (26.9) | 12.3 (29.2) | 0.142 (17.3)
Ctrough (microgram per mL) | 2.61 (35.2) | 0.096 (37.4) | NA
CV=Coefficient of Variation; NA=Not Applicable

Specific Populations

Patients with Renal Impairment

No clinically relevant differences in the pharmacokinetics of BIC, TAF, or its metabolite tenofovir were observed between participants with severe renal impairment (estimated creatinine clearance of 15 to less than 30 mL/min, by Cockcroft-Gault method) and healthy participants in Phase 1 studies. In a separate Phase 1 study of FTC alone, FTC exposures were increased in participants with severe renal impairment.

The pharmacokinetics of BIC, FTC and TAF were evaluated in a subset of HIV-1 infected virologically-suppressed participants with ESRD (estimated creatinine clearance less than 15 mL/min, by Cockcroft-Gault method) receiving chronic hemodialysis in Trial 1825. The pharmacokinetics of TAF were similar between healthy participants and participants with ESRD receiving chronic hemodialysis; increases in FTC and tenofovir exposures in participants with ESRD were not considered clinically relevant. Median (minimum, maximum) BIC Ctrough values in participants (n=7) with ESRD who received BIKTARVY were 846 ng/mL (288, 1810) compared to 2540 ng/mL (757, 6499) in participants (N=584) with normal renal function. Despite significantly lower BIC Ctrough values in the virologically-suppressed ESRD population, virologic suppression was maintained [see Use in Specific Populations (8.6), and Clinical Studies (14.3)].

Patients with Hepatic Impairment

Bictegravir: Clinically relevant changes in the pharmacokinetics of BIC were not observed in participants with moderate (Child-Pugh Class B) hepatic impairment.

Emtricitabine: The pharmacokinetics of FTC has not been studied in participants with hepatic impairment; however, FTC is not significantly metabolized by liver enzymes, so the impact of hepatic impairment should be limited.

Tenofovir Alafenamide: Clinically relevant changes in the pharmacokinetics of TAF or its metabolite tenofovir were not observed in participants with mild or moderate (Child-Pugh Class A and B) hepatic impairment [see Use in Specific Populations (8.7)].

Hepatitis B and/or Hepatitis C Virus Coinfection

The pharmacokinetics of BIC, FTC, and TAF have not been evaluated in participants with hepatitis B and/or C virus.

Geriatric Patients

The pharmacokinetics of BIC, FTC, and TAF have not been fully evaluated in the elderly (65 years of age and older). Population pharmacokinetics analysis of HIV-infected participants in Phase 3 trials of BIKTARVY showed that age did not have a clinically relevant effect on exposures of BIC and TAF up to 74 years of age [see Use in Specific Populations (8.5)].

Pediatric Patients

Mean BIC Ctrough was lower in 50 pediatric patients aged 12 to less than 18 years and weighing at least 35 kg who received BIKTARVY in Trial 1474 relative to adults following administration of BIKTARVY, but was not considered clinically significant based on exposure-response relationships; exposures of FTC and TAF in these pediatric patients were similar to those in adults (Table 6).

Table 6 Multiple Dose PK Parameters of BIC, FTC, and TAF Following Oral Administration of BIKTARVY in Pediatric Participants with HIV-1 Aged 12 to less than 18 years
Parameter Mean (CV%) | Bictegravir [From Population PK analysis of cohort 1 of Trial 1474 (n=50 for BIC; n=49 for TAF).] | Emtricitabine [From Intensive PK analysis of cohort 1 of Trial 1474 (n=24).] | Tenofovir Alafenamide
Cmax (microgram per mL) | 6.24 (27.1) | 2.69 (34.0) | 0.133 (70.2)
AUCtau (microgram•h per mL) | 89.1 (31.0) | 13.6 (21.7) | 0.196 (50.3)
Ctrough (microgram per mL) | 1.78 (44.4) | 0.064 (25.0) | NA
CV=Coefficient of Variation; NA=Not Applicable

Mean BIC Cmax, and exposures of FTC and TAF (AUCtau and Cmax) achieved in 50 pediatric patients between the ages of 6 to less than 12 years and weighing at least 25 kg, and in 22 pediatric patients at least 2 years of age and weighing at least 14 to less than 25 kg who received BIKTARVY in Trial 1474 were higher than exposures in adults; however, the increases were not considered clinically significant as the safety profiles were similar in adult and pediatric patients (Tables 7 and 8) [see Use in Specific Populations (8.4)].

Table 7 Multiple Dose PK Parameters of BIC, FTC, and TAF Following Oral Administration of BIKTARVY in Pediatric Participants with HIV-1 Aged 6 to less than 12 years
Parameter Mean (CV%) | Bictegravir [From Population PK analysis of cohort 2 of Trial 1474 (n=50 for BIC; n=47 for TAF).] | Emtricitabine [From Intensive PK analysis of cohort 2 of Trial 1474 (n=25 except n=24 for Ctrough).] | Tenofovir Alafenamide
Cmax (microgram per mL) | 9.46 (24.3) | 3.89 (31.0) | 0.205 (44.6)
AUCtau (microgram•h per mL) | 128 (27.8) | 17.6 (36.9) | 0.278 (40.3)
Ctrough (microgram per mL) | 2.36 (39.0) | 0.227 (323) | NA
CV=Coefficient of Variation; NA=Not Applicable

Table 8 Multiple Dose PK Parameters of BIC, FTC, and TAF Following Oral Administration of BIKTARVY in Pediatric Participants with HIV-1 at Least 2 Years of Age [Cohort 3 of Trial 1474 enrolled pediatric participants from 3 to 9 years of age.] and Weighing at Least 14 to Less than 25 kg
Parameter Mean (CV%) | Bictegravir [From Population PK analysis of cohort 3 of Trial 1474 (n=22).] | Emtricitabine [From Intensive PK analysis of cohort 3 of Trial 1474 (n=12 except n=11 for Ctrough for FTC).] | Tenofovir Alafenamide
Cmax (microgram per mL) | 9.15 (44.8) | 3.85 (34.7) | 0.414 (31.0)
AUCtau (microgram•h per mL) | 126 (42.4) | 15.0 (21.9) | 0.305 (42.6)
Ctrough (microgram per mL) | 2.43 (40.1) | 0.210 (243) | NA
CV=Coefficient of Variation; NA=Not Applicable

Race and Gender

No clinically relevant changes in the pharmacokinetics of BIC, FTC, and TAF were observed based on gender or race.

Pregnancy

Plasma exposures (Ctrough and AUCtau) of BIC, FTC, and TAF after intake of BIKTARVY 50 mg/200 mg/25 mg were lower during pregnancy as compared to postpartum (Table 9). The exposure changes during pregnancy are not considered clinically significant in virologically suppressed pregnant individuals [see Drug Interactions (7.5)].

Table 9 Steady-state PK Parameters of BIC, FTC, and TAF Following Oral Administration of BIKTARVY in Virologically-Suppressed Pregnant Adults with HIV-1 in the Second and Third Trimesters and Week 12 Postpartum
Parameter Mean (%CV) | Second Trimester (N=21) | Third Trimester (N=30) | Week 12 Postpartum (N=32)
Bictegravir
Cmax (microgram per mL) | 5.82 (30.1) | 5.37 (25.9) | 11.03 (24.9)
AUCtau (microgram•h per mL) | 62.8 (32.2) | 60.2 (29.1) | 148.3 (28.5)
Unbound AUCtau [Calculated by correcting the individual AUCtau estimates by the % unbound fraction.] (microgram•h per mL) | 0.224 (42.0) | 0.219 (33.9) | 0.374 (32.2)
Ctrough (microgram per mL) | 1.05 (45.2) | 1.07 (41.7) | 3.64 (34.1)
Emtricitabine
Cmax (microgram per mL) | 2.64 (36.6) | 2.59 (26.5) | 3.36 (26.9)
AUCtau (microgram•h per mL) | 10.3 (20.0) | 10.4 (20.3) | 15.3 (21.9)
Ctrough (microgram per mL) | 0.06 (103.9) | 0.05 (27.2) | 0.08 (33.7)
Tenofovir Alafenamide
Cmax (microgram per mL) | 0.33 (52.1) | 0.27 (42.1) | 0.49 (52.5)
AUCtau (microgram•h per mL) | 0.24 (45.6) | 0.21 (45.0) | 0.30 (31.8)
Unbound AUCtau (microgram•h per mL) | 0.015 (28.2) | 0.016 (28.4) | 0.017 (23.4)
CV = Coefficient of Variation; NA = Not Available

Drug Interaction Studies

As BIKTARVY is a complete regimen for the treatment of HIV-1 infection, comprehensive information regarding potential drug-drug interactions with other antiretroviral agents is not provided.

BIC is a substrate of CYP3A and UGT1A1.

BIC is an inhibitor of OCT2 and MATE1. At clinically relevant concentrations, BIC is not an inhibitor of hepatic transporters OATP1B1, OATP1B3, OCT1, BSEP, renal transporters OAT1 and OAT3, or CYP (including CYP3A) or UGT1A1 enzymes.

TAF is a substrate of P-gp and BCRP.

At clinically relevant concentrations, TAF is not an inhibitor of drug transporters P-gp, BCRP, hepatic transporters OATP1B1, OATP1B3, OCT1, BSEP, renal transporters OAT1, OAT3, OCT2, MATE1, or CYP (including CYP3A) or UGT1A1 enzymes.

Drug interaction studies were conducted with BIKTARVY or its components. Tables 10 and 11 summarize the pharmacokinetic effects of other drugs on BIC and TAF, respectively. Table 12 summarizes the pharmacokinetic effects of BIKTARVY or its components on other drugs.

Effect of Other Drugs on BIKTARVY Components

Table 10 Effect of Other Drugs on BIC [All interaction studies conducted in healthy volunteers.]
Coadministered Drug | Dose of Coadministered Drug (mg) | BIC (mg) | Mean Ratio of BIC Pharmacokinetic Parameters (90% CI); No effect = 1.00
Coadministered Drug | Dose of Coadministered Drug (mg) | BIC (mg) | Cmax | AUC | Cmin
Ledipasvir/Sofosbuvir (fed) | 90/400 once daily | 75 once daily | 0.98 (0.94, 1.03) | 1.00 (0.97, 1.03) | 1.04 (0.99, 1.09)
Rifabutin (fasted) | 300 once daily | 75 once daily | 0.80 (0.67, 0.97) | 0.62 (0.53, 0.72) | 0.44 (0.37, 0.52)
Rifampin (fed) | 600 once daily | 75 single dose | 0.72 (0.67, 0.78) | 0.25 (0.22, 0.27) | NA
Sofosbuvir/ velpatasvir/ voxilaprevir (fed) | 400/100/100+100 voxilaprevir [Study conducted with additional voxilaprevir 100 mg to achieve voxilaprevir exposures expected in HCV-infected patients.] once daily | 50 once daily | 0.98 (0.94, 1.01) | 1.07 (1.03, 1.10) | 1.10 (1.05, 1.17)
Voriconazole (fasted) | 300 twice daily | 75 single dose | 1.09 (0.96, 1.23) | 1.61 (1.41, 1.84) | NA
Maximum strength antacid (simultaneous administration, fasted) | 20 mL [Maximum strength antacid contained 80 mg aluminum hydroxide, 80 mg magnesium hydroxide, and 8 mg simethicone, per mL.] single dose (oral) | 50 single dose | 0.20 (0.16, 0.24) | 0.21 (0.18, 0.26) | NA
Maximum strength antacid (2 h after BIKTARVY fasted) | 20 mL single dose (oral) | 50 single dose | 0.93 (0.88, 1.00) | 0.87 (0.81, 0.93) | NA
Maximum strength antacid (2 h before BIKTARVY fasted) | 20 mL single dose (oral) | 50 single dose | 0.42 (0.33, 0.52) | 0.48 (0.38, 0.59) | NA
Maximum strength antacid (simultaneous administration, fed [Reference treatment administered under fasted conditions.]) | 20 mL single dose (oral) | 50 single dose | 0.51 (0.43, 0.62) | 0.53 (0.44, 0.64) | NA
Calcium carbonate (simultaneous administration, fasted) | 1200 single dose | 50 single dose | 0.58 (0.51, 0.67) | 0.67 (0.57, 0.78) | NA
Calcium carbonate (simultaneous administration, fed) | 1200 single dose | 50 single dose | 0.90 (0.78, 1.03) | 1.03 (0.89, 1.20) | NA
Ferrous fumarate (simultaneous administration, fasted) | 324 single dose | 50 single dose | 0.29 (0.26, 0.33) | 0.37 (0.33, 0.42) | NA
Ferrous fumarate (simultaneous administration, fed) | 324 single dose | 50 single dose | 0.75 (0.65, 0.87) | 0.84 (0.74, 0.95) | NA
NA= Not Applicable

Table 11 Effect of Other Drugs on TAF [All interaction studies conducted in healthy volunteers.]
Coadministered Drug | Dose of Coadministered Drug (mg) | Tenofovir Alafenamide (mg) | Mean Ratio of Tenofovir Alafenamide Pharmacokinetic Parameters (90% CI); No effect = 1.00
Coadministered Drug | Dose of Coadministered Drug (mg) | Tenofovir Alafenamide (mg) | Cmax | AUC | Cmin
Carbamazepine | 300 twice daily | 25 single dose [Study conducted with emtricitabine/tenofovir alafenamide.] | 0.43 (0.36, 0.51) | 0.46 (0.40, 0.54) | NA
Ledipasvir/sofosbuvir | 90/400 once daily | 25 once daily | 1.17 (1.00, 1.38) | 1.27 (1.19, 1.34) | NA
Sofosbuvir/ velpatasvir/ voxilaprevir | 400/100/100 +100 voxilaprevir [Study conducted with additional voxilaprevir 100 mg to achieve voxilaprevir exposures expected in HCV-infected patients.] once daily | 25 once daily | 1.28 (1.09, 1.51) | 1.57 (1.44, 1.71) | NA
NA= Not Applicable

Effect of BIKTARVY Components on Other Drugs

Table 12 Effect of Components of BIKTARVY on Other Drugs [All interaction studies conducted in healthy volunteers.]
Coadministered Drug | Dose of Coadministered Drug (mg) | BIC (mg) | TAF (mg) | Mean Ratio of Coadministered Drug Pharmacokinetic Parameters (90% CI); No effect = 1.00
Coadministered Drug | Dose of Coadministered Drug (mg) | BIC (mg) | TAF (mg) | Cmax | AUC | Cmin
Ledipasvir | 90/400 once daily | 75 once daily | 25 once daily | 0.85 (0.81, 0.90) | 0.87 (0.83, 0.92) | 0.90 (0.84, 0.96)
Sofosbuvir | 90/400 once daily | 75 once daily | 25 once daily | 1.11 (1.00, 1.24) | 1.07 (1.01, 1.13) | NA
GS-331007 [The predominant circulating nucleoside metabolite of sofosbuvir.] | 90/400 once daily | 75 once daily | 25 once daily | 1.10 (1.07, 1.13) | 1.11 (1.08, 1.14) | 1.02 (0.99, 1.06)
Metformin | 500 twice daily | 50 once daily | 25 once daily | 1.28 (1.21, 1.36) | 1.39 (1.31, 1.48) | 1.36 (1.21, 1.53)
Midazolam | 2 single dose | 50 once daily | 25 once daily | 1.03 (0.87, 1.23) | 1.15 (1.00, 1.31) | NA
Norelgestromin | norgestimate 0.180/0.215/0.250 once daily / ethinyl estradiol 0.025 once daily | 75 once daily | - | 1.23 (1.14, 1.32) | 1.08 (1.05, 1.10) | 1.10 (1.05, 1.15)
Norgestrel | norgestimate 0.180/0.215/0.250 once daily / ethinyl estradiol 0.025 once daily | 75 once daily | - | 1.15 (1.10, 1.21) | 1.13 (1.07, 1.19) | 1.14 (1.06, 1.22)
Ethinyl estradiol | norgestimate 0.180/0.215/0.250 once daily / ethinyl estradiol 0.025 once daily | 75 once daily | - | 1.15 (1.03, 1.27) | 1.04 (0.99, 1.10) | 1.05 (0.95, 1.14)
Norelgestromin | norgestimate 0.180/0.215/0.250 once daily / ethinyl estradiol 0.025 once daily | - | 25 once daily [Study conducted with emtricitabine/tenofovir alafenamide.] | 1.17 (1.07,1.26) | 1.12 (1.07,1.17) | 1.16 (1.08, 1.24)
Norgestrel | norgestimate 0.180/0.215/0.250 once daily / ethinyl estradiol 0.025 once daily | - | 25 once daily [Study conducted with emtricitabine/tenofovir alafenamide.] | 1.10 (1.02, 1.18) | 1.09 (1.01, 1.18) | 1.11 (1.03, 1.20)
Ethinyl estradiol | norgestimate 0.180/0.215/0.250 once daily / ethinyl estradiol 0.025 once daily | - | 25 once daily [Study conducted with emtricitabine/tenofovir alafenamide.] | 1.22 (1.15, 1.29) | 1.11 (1.07, 1.16) | 1.02 (0.92, 1.12)
Sertraline | 50 single dose | - | 10 once daily [Study conducted with elvitegravir/cobicistat/emtricitabine/tenofovir alafenamide.] | 1.14 (0.94, 1.38) | 0.93 (0.77, 1.13) | NA
Sofosbuvir | 400/100/100+100 [Study conducted with additional voxilaprevir 100 mg to achieve voxilaprevir exposures expected in HCV-infected patients.] once daily | 50 once daily | 25 once daily | 1.14 (1.04,1.25) | 1.09 (1.02, 1.15) | NA
GS-331007 | 400/100/100+100 [Study conducted with additional voxilaprevir 100 mg to achieve voxilaprevir exposures expected in HCV-infected patients.] once daily | 50 once daily | 25 once daily | 1.03 (0.99,1.06) | 1.03 (1.00,1.06) | 1.01 (0.98, 1.05)
Velpatasvir | 400/100/100+100 [Study conducted with additional voxilaprevir 100 mg to achieve voxilaprevir exposures expected in HCV-infected patients.] once daily | 50 once daily | 25 once daily | 0.96 (0.91,1.01) | 0.96 (0.90, 1.02) | 0.94 (0.88, 1.01)
Voxilaprevir | 400/100/100+100 [Study conducted with additional voxilaprevir 100 mg to achieve voxilaprevir exposures expected in HCV-infected patients.] once daily | 50 once daily | 25 once daily | 0.90 (0.76, 1.06) | 0.91 (0.80, 1.03) | 0.97 (0.88, 1.06)
NA= Not Applicable

12.4 Microbiology

Mechanism of Action

Bictegravir: BIC inhibits the strand transfer activity of HIV-1 integrase (integrase strand transfer inhibitor; INSTI), an HIV-1 encoded enzyme that is required for viral replication. Inhibition of integrase prevents the integration of linear HIV-1 DNA into host genomic DNA, blocking the formation of the HIV-1 provirus and propagation of the virus.

Emtricitabine: FTC, a synthetic nucleoside analog of cytidine, is phosphorylated by cellular enzymes to form emtricitabine 5'-triphosphate. Emtricitabine 5'-triphosphate inhibits the activity of the HIV-1 RT by competing with the natural substrate deoxycytidine 5'-triphosphate and by being incorporated into nascent viral DNA which results in chain termination. Emtricitabine 5′-triphosphate is a weak inhibitor of mammalian DNA polymerases α, β, Ɛ, and mitochondrial DNA polymerase γ.

Tenofovir Alafenamide: TAF is a phosphonamidate prodrug of tenofovir (2′-deoxyadenosine monophosphate analog). Plasma exposure to TAF allows for permeation into cells and then TAF is intracellularly converted to tenofovir through hydrolysis by cathepsin A. Tenofovir is subsequently phosphorylated by cellular kinases to the active metabolite tenofovir diphosphate. Tenofovir diphosphate inhibits HIV-1 replication through incorporation into viral DNA by the HIV RT, which results in DNA chain-termination. Tenofovir diphosphate is a weak inhibitor of mammalian DNA polymerases that include mitochondrial DNA polymerase γ and there is no evidence of toxicity to mitochondria in cell culture.

Antiviral Activity in Cell Culture

The triple combination of BIC, FTC, and TAF was not antagonistic with respect to antiviral activity in cell culture.

Bictegravir: The antiviral activity of BIC against laboratory and clinical isolates of HIV-1 was assessed in lymphoblastoid cell lines, PBMCs, primary monocyte/macrophage cells, and CD4+ T-lymphocytes. In MT-4 cells (human lymphoblastoid T-cell line) acutely infected with HIV-1 IIIB, the mean 50% effective concentration (EC50) was 2.4±0.4 nM, and the protein-adjusted EC95 value was 361 nM (0.162 micrograms per mL). BIC displayed antiviral activity in activated PBMCs against clinical isolates of HIV-1 representing groups M, N, and O, including subtypes A, B, C, D, E, F, and G, with a median EC50 value of 0.55 nM (range <0.05 to 1.71 nM). The EC50 value against a single HIV-2 isolate was 1.1 nM.

Emtricitabine: The antiviral activity of FTC against laboratory and clinical isolates of HIV-1 was assessed in T lymphoblastoid cell lines, the MAGI-CCR5 cell line, and PBMCs. In PBMCs acutely infected with HIV-1 subtypes A, B, C, D, E, F, and G, the median EC50 value for FTC was 9.5 nM (range 1 to 30 nM) and against HIV-2 was 7 nM.

Tenofovir Alafenamide: The antiviral activity of TAF against laboratory and clinical isolates of HIV-1 subtype B was assessed in lymphoblastoid cell lines, PBMCs, primary monocyte/macrophage cells and CD4-T lymphocytes. The EC50 values for TAF ranged from 2.0 to 14.7 nM. TAF displayed antiviral activity in cell culture against all HIV-1 groups (M, N, O), including subtypes A, B, C, D, E, F, and G (EC50 values ranged from 0.1 to 12 nM) and strain specific activity against HIV-2 (EC50 values ranged from 0.9 to 2.6 nM).

Resistance

In Cell Culture

Bictegravir: HIV-1 isolates with reduced susceptibility to BIC have been selected in cell culture. In one selection with BIC, a virus pool emerged expressing amino acid substitutions M50I and R263K in the HIV-1 integrase. M50I, R263K, and M50I+R263K substitutions, when introduced into a wild-type virus by site-directed mutagenesis, conferred 1.3-, 2.2-, and 2.9-fold reduced susceptibility to BIC, respectively. In a second selection, emergence of amino acid substitutions T66I and S153F was detected, and 0.4-, 1.9-, and 0.5-fold reductions in BIC susceptibility were observed with T66I, S153F, and T66I+S153F, respectively. In addition, S24G and E157K substitutions emerged during the selection process.

Emtricitabine: HIV-1 isolates with reduced susceptibility to FTC were selected in cell culture and in participants treated with FTC. Reduced susceptibility to FTC was associated with M184V or I substitutions in HIV-1 RT.

Tenofovir Alafenamide: HIV-1 isolates with reduced susceptibility to TAF were selected in cell culture. HIV-1 isolates selected by TAF expressed a K65R substitution in HIV-1 RT, sometimes in the presence of S68N or L429I substitutions; in addition, a K70E substitution in HIV-1 RT was observed.

In Clinical Trials

In Participants with No Antiretroviral Treatment History: Pooled results of genotypic resistance analyses were performed on paired baseline and on-treatment HIV-1 isolates from participants receiving BIKTARVY in Trials 1489 and 1490 through Week 144 of the double-blind phase (N=634) or Week 96 of the extension phase (n=1025) [see Clinical Studies (14.2)] who had HIV-1 RNA greater than or equal to 200 copies/mL at the time of confirmed virologic failure or early study drug discontinuation. In the final resistance analysis population, no specific amino acid substitutions emerged consistently in the 11 participants with treatment failure and with evaluable genotypic resistance data and failed to establish an association with genotypic BIC resistance. There were no treatment-emergent NRTI resistance-associated substitutions detected in the 11 evaluated treatment failure isolates. Phenotypic resistance analyses of failure isolates found fold-changes in drug susceptibility below the biological or clinical cutoffs for BIC, FTC, and TFV, compared to wild-type reference HIV-1.

In Virologically-Suppressed Adult participants: In 2 of the switch trials, Trials 1844 and 1878, of virologically suppressed HIV-1 infected participants (n=572), only one participants with virologic rebound in the resistance analysis population had IN genotypic and phenotypic data, and 2 rebounders had RT genotypic and phenotypic data. No participants had HIV-1 with treatment-emergent genotypic or phenotypic resistance to BIC, FTC, or TAF. In Trial 4030, no participants receiving BIKTARVY had treatment-emergent phenotypic resistance to BIC, FTC, or TAF.

In Virologically-Suppressed Pediatric Participants: In Trial 1474 [see Clinical Studies (14.4)], two of 50 participants in cohort 1 were evaluated for the development of resistance through Week 48; no amino acid substitutions known to be associated with resistance to BIC, FTC, or TFV were detected. No participants in cohort 2 or 3 met the criteria for resistance analyses through Week 24.

Cross-Resistance

Bictegravir: Cross-resistance has been observed among INSTIs. The susceptibility of BIC was tested against 64 clinical isolates expressing known INSTI resistance-associated substitutions listed by IAS-USA (20 with single substitutions and 44 with 2 or more substitutions). Isolates with a single INSTI-resistance substitution including E92Q, T97A, Y143C/R, Q148R, and N155H showed less than 2-fold reduced susceptibility to BIC. All isolates (n=14) with more than 2.5-fold reduced susceptibility to BIC (above the biological cutoff for BIC) contained G140A/C/S and Q148H/R/K substitutions; the majority (64.3%, 9/14) had a complex INSTI resistance pattern with an additional INSTI-resistance substitution L74M, T97A, or E138A/K. Of those evaluated isolates containing G140A/C/S and Q148H/R/K substitutions in the absence of additional INSTI-resistance substitutions, 38.5% (5/13) showed more than 2.5-fold reduction. In addition, site-directed mutant viruses with G118R (dolutegravir and raltegravir treatment-emergent substitution) and G118R+T97A had 3.4- and 2.8-fold reduced susceptibility to BIC, respectively.

BIC demonstrated equivalent antiviral activity with less than 2-fold reductions in susceptibility against HIV-1 variants expressing substitutions associated with resistance to NNRTIs, NRTIs, and PIs, compared with the wild-type virus.

Emtricitabine: Cross-resistance has been observed among NRTIs. FTC-resistant viruses with an M184V/I substitution in HIV-1 RT were cross-resistant to lamivudine. HIV-1 isolates containing the K65R RT substitution, selected in vivo by abacavir, didanosine, and tenofovir, demonstrated reduced susceptibility to inhibition by FTC.

Tenofovir Alafenamide: Cross-resistance has been observed among NRTIs. Tenofovir resistance substitutions K65R and K70E result in reduced susceptibility to abacavir, didanosine, emtricitabine, lamivudine, and tenofovir. HIV-1 with multiple thymidine analog substitutions (M41L, D67N, K70R, L210W, T215F/Y, K219Q/E/N/R), or multinucleoside resistant HIV-1 with a T69S double insertion mutation or with a Q151M substitution complex including K65R, showed reduced susceptibility to TAF in cell culture.

13 NONCLINICAL TOXICOLOGY

13.1 Carcinogenesis, Mutagenesis, Impairment of Fertility

Bictegravir

BIC was not carcinogenic in a 6-month rasH2 transgenic mouse study at doses of up to 100 mg/kg/day in males and 300 mg/kg/day in females. BIC was not carcinogenic in a 2-year rat study at doses up to 300 mg/kg/day, which resulted in exposures of approximately 31 times the exposure in humans at the recommended dose of BIKTARVY.

BIC was not genotoxic in the reverse mutation bacterial test (Ames test), mouse lymphoma or rat micronucleus assays.

BIC did not affect fertility, reproductive performance or embryonic viability in male and female rats at 29 times higher exposures (AUC) than in humans at the recommended dose of BIKTARVY.

Emtricitabine

In long-term carcinogenicity studies of FTC, no drug-related increases in tumor incidence were found in mice at doses up to 750 mg per kg per day (25 times the human systemic exposure at the recommended dose of BIKTARVY) or in rats at doses up to 600 mg per kg per day (30 times the human systemic exposure at the recommended dose of BIKTARVY).

FTC was not genotoxic in the reverse mutation bacterial test (Ames test), mouse lymphoma or mouse micronucleus assays.

FTC did not affect fertility in male rats at approximately 140 times or in male and female mice at approximately 60 times higher exposures (AUC) than in humans given the recommended dose of BIKTARVY. Fertility was normal in the offspring of mice exposed daily from before birth (in utero) through sexual maturity at daily exposures (AUC) of approximately 60 times higher than human exposures at the recommended dose of BIKTARVY.

Tenofovir Alafenamide

Since TAF is rapidly converted to tenofovir and a lower tenofovir exposure in rats and mice was observed after TAF administration compared to TDF administration, carcinogenicity studies were conducted only with TDF. Long-term oral carcinogenicity studies of TDF in mice and rats were carried out at exposures up to approximately 10 times (mice) and 4 times (rats) those observed in humans following a 300 mg dose of TDF. The tenofovir exposure in these studies was approximately 151 times (mice) and 51 times (rat) those observed in humans after administration of the daily recommended dose of BIKTARVY. At the high dose in female mice, liver adenomas were increased at tenofovir exposures approximately 151 times the exposure observed in humans at the recommended dose of BIKTARVY. In rats, the study was negative for carcinogenic findings.

TAF was not genotoxic in the reverse mutation bacterial test (Ames test), mouse lymphoma or rat micronucleus assays.

There were no effects on fertility, mating performance or early embryonic development when TAF was administered to male rats at a dose equivalent to 155 times the human dose of BIKTARVY based on body surface area comparisons for 28 days prior to mating and to female rats for 14 days prior to mating through Day 7 of gestation.

13.2 Animal Toxicology and/or Pharmacology

Minimal to slight infiltration of mononuclear cells in the posterior uvea was observed in dogs with similar severity after three and nine month administration of TAF; reversibility was seen after a three month recovery period. No eye toxicity was observed in the dog at systemic exposures of 7 (TAF) and 14 (tenofovir) times the exposure seen in humans with the recommended daily dose of BIKTARVY.

14 CLINICAL STUDIES

14.1 Description of Clinical Trials

The efficacy and safety of BIKTARVY were evaluated in the trials summarized in Table 13.

Table 13 Trials Conducted with BIKTARVY in Participants with HIV-1
Trial | Population | Trial Arms (N) | Timepoint (Week)
Trial 1489 [Randomized, double blind, active controlled trial.] (NCT 02607930) | Adults with no antiretroviral treatment history | BIKTARVY (314) ABC/DTG/3TC (315) | 144 + 96 (OLE) [144-week double-blind active controlled phase followed by an extension phase in which 1025 participants from Trials 1489 and 1490 received open-label BIKTARVY for 96 weeks.]
Trial 1490 (NCT 02607956) | Adults with no antiretroviral treatment history | BIKTARVY (320) DTG + FTC/TAF(325) | 144 + 96 (OLE)
Trial 1844 (NCT 02603120) | Virologically-suppressed [HIV-1 RNA less than 50 copies per mL.] adults | BIKTARVY (282) ABC/DTG/3TC (281) | 48
Trial 1878 [Randomized, open-label, active controlled trial.] (NCT 02603107) | Virologically-suppressed [HIV-1 RNA less than 50 copies per mL.] adults | BIKTARVY (290) ATV or DRV (with cobicistat or ritonavir) plus either FTC/TDF or ABC/3TC (287) | 48
Trial 4030 (NCT 03110380) | Virologically-suppressed [HIV-1 RNA less than 50 copies per mL.] adults | BIKTARVY (284 [47 with M184V/I]) DTG plus FTC/TAF (281 [34 with M184V/I]) | 48
Trial 1825 [Open-label trial.] (NCT 02600819) | Virologically-suppressed adults with ESRD [End stage renal disease (estimated creatinine clearance of less than 15 mL/min by Cockcroft-Gault method).] receiving chronic hemodialysis | FTC+TAF in combination with elvitegravir and cobicistat as a fixed-dose combination (55). In an extension phase of Trial 1825, 10 virologically-suppressed participants switched to BIKTARVY. | 48 [Participants received FTC+TAF in combination with elvitegravir and cobicistat for 96 weeks, followed by an extension phase in which 10 participants received BIKTARVY for 48 weeks.]
Trial 4449 (NCT 03405935) | Virologically-suppressed adults aged 65 years and over | BIKTARVY (86) | 48
Trial 1474 (cohort 1) (NCT 02881320) | Virologically-suppressed adolescents between the ages of 12 to less than 18 years (at least 35 kg) | BIKTARVY (50) | 48
Trial 1474 (cohort 2) (NCT 02881320) | Virologically-suppressed children between the ages of 6 to less than 12 years (at least 25 kg) | BIKTARVY (50) | 24
Trial 1474 (cohort 3) (NCT 02881320) | Virologically-suppressed children at least 2 years of age (at least 14 to less than 25 kg) | BIKTARVY (22) | 24
OLE = open-label extension

14.2 Clinical Trial Results in Adults with HIV-1 and No Antiretroviral Treatment History

In Trial 1489, adults were randomized in a 1:1 ratio to receive either BIKTARVY (containing 50 mg of BIC, 200 mg of FTC, and 25 mg of TAF) (N=314) or ABC/DTG/3TC (600 mg/50 mg/300 mg) (N=315) once daily. In Trial 1490, participants were randomized in a 1:1 ratio to receive either BIKTARVY (N=320) or DTG + FTC/TAF (50 mg + 200 mg/25 mg) (N=325) once daily.

In Trial 1489, the mean age was 34 years (range 18–71), 90% were male, 57% were White, 36% were Black, and 3% were Asian. 22% of patients identified as Hispanic/Latino. The mean baseline plasma HIV-1 RNA was 4.4 log10 copies/mL (range 1.3–6.5). The mean baseline CD4+ cell count was 464 cells per mm^3 (range 0–1424) and 11% had CD4+ cell counts less than 200 cells per mm^3. 16% of participants had baseline viral loads greater than 100,000 copies per mL.

In Trial 1490, the mean age was 37 years (range 18–77), 88% were male, 59% were White, 31% were Black, and 3% were Asian. 25% of patients identified as Hispanic/Latino. The mean baseline plasma HIV-1 RNA was 4.4 log10 copies/mL (range 2.3–6.6). The mean baseline CD4+ cell count was 456 cells per mm^3 (range 2–1636) and 12% had CD4+ cell counts less than 200 cells per mm^3. 19% of participants had baseline viral loads greater than 100,000 copies per mL.

In both trials, participants were stratified by baseline HIV-1 RNA (less than or equal to 100,000 copies per mL, greater than 100,000 copies per mL to less than or equal to 400,000 copies per mL, or greater than 400,000 copies per mL), by CD4 count (less than 50 cells per mm^3, 50-199 cells per mm^3, or greater than or equal to 200 cells per mm^3), and by region (US or ex-US).

Treatment outcomes of Trials 1489 and 1490 through Week 144 are presented in Table 14.

Table 14 Virologic Outcomes of Randomized Treatment in Trials 1489 and 1490 at Week 144 [Week 144 window was between Day 967 and 1050 (inclusive).] in Adults with No Antiretroviral Treatment History
 | Trial 1489 |  | Trial 1490
 | BIKTARVY (N=314) | ABC/DTG/3TC (N=315) | BIKTARVY (N=320) | DTG + FTC/TAF (N=325)
HIV-1 RNA < 50 copies/mL | 82% | 84% | 82% | 84%
Treatment Difference (95% CI) BIKTARVY vs. Comparator | -2.6% (-8.5% to 3.4%) |  | -1.9% (-7.8% to 3.9%)
HIV-1 RNA ≥ 50 copies/mL [Includes participants who had ≥ 50 copies/mL in the Week 144 window; participants who discontinued early due to lack or loss of efficacy; participants who discontinued for reasons other than an adverse event (AE), death or lack or loss of efficacy and at the time of discontinuation had a viral value of ≥ 50 copies/mL.] | 1% | 3% | 5% | 3%
No Virologic Data at Week 144 Window | 18% | 13% | 13% | 13%
Discontinued Study Drug Due to AE or Death [Includes participants who discontinued due to AE or death at any time point from Day 1 through the time window if this resulted in no virologic data on treatment during the specified window.] | 1% | 2% | 3% | 3%
Discontinued Study Drug Due to Other Reasons and Last Available HIV-1 RNA <50 copies/mL [Includes participants who discontinued for reasons other than an AE, death, or lack or loss of efficacy, e.g., withdrew consent, loss to follow-up, etc.] | 16% | 11% | 11% | 9%
Missing Data During Window but on Study Drug | 1% | <1% | 0% | 1%

Treatment outcomes were similar across subgroups by age, sex, race, baseline viral load, and baseline CD4+ cell count.

In Trials 1489 and 1490, the mean increase from baseline in CD4+ count at Week 144 was 299 and 317 cells per mm^3 in the BIKTARVY and ABC/DTG/3TC groups, respectively, and 278 and 289 cells per mm^3 in the BIKTARVY and DTG + FTC/TAF groups, respectively.

14.3 Use in Individuals with an Antiretroviral Treatment History and Not Virologically-Suppressed

Use of BIKTARVY in those with an antiretroviral treatment history and not virologically suppressed is supported by a scientific rationale that this population is expected to have similar virologic response rates to those with no history of antiretroviral treatment provided that the virus is susceptible to the individual components of the regimen. Because limited clinical trial data are available supporting the efficacy of BIKTARVY in patients with baseline INSTI resistance substitutions, this indication states use in individuals with an antiretroviral treatment history and who are not virologically suppressed with no evidence of known or suspected substitutions associated with resistance to the INSTI class, rather than only to bictegravir. Additionally, this indication states the individuals should have no known or suspected substitutions associated with resistance to emtricitabine, or tenofovir [see Clinical Studies (14.2 and 14.5)].

14.4 Clinical Trial Results in Adults with Virologically-Suppressed HIV-1 Who Switched to BIKTARVY

In Trial 1844, the efficacy and safety of switching from a regimen of DTG + ABC/3TC or ABC/DTG/3TC to BIKTARVY were evaluated in a randomized, double-blind trial of virologically-suppressed (HIV-1 RNA less than 50 copies per mL) HIV-1 infected adults (N=563, randomized and dosed). Participants must have been stably suppressed (HIV-1 RNA less than 50 copies per mL) on their baseline regimen for at least 3 months prior to trial entry and had no history of treatment failure. Participants were randomized in a 1:1 ratio to either switch to BIKTARVY (containing 50 mg of BIC, 200 mg of FTC, and 25 mg of TAF) at baseline (N=282), or stay on their baseline antiretroviral regimen (N=281). Participants had a mean age of 45 years (range 20–71), 89% were male, 73% were White, and 22% were Black. 17% of participants identified as Hispanic/Latino. The mean baseline CD4+ cell count was 723 cells per mm^3 (range 124–2444).

In Trial 1878, the efficacy and safety of switching from either ABC/3TC or FTC/TDF (200/300 mg) plus ATV or DRV (given with either cobicistat or ritonavir) to BIKTARVY (containing 50 mg of BIC, 200 mg of FTC, and 25 mg of TAF) were evaluated in a randomized, open-label study of virologically-suppressed HIV-1 infected adults (N=577, randomized and dosed). Participants must have been stably suppressed on their baseline regimen for at least 6 months, must not have been previously treated with any INSTI, and had no history of treatment failure. Participants were randomized in a 1:1 ratio to either switch to BIKTARVY (N=290) or stay on their baseline antiretroviral regimen (N=287). Participants had a mean age of 46 years (range 20–79), 83% were male, 66% were White, and 26% were Black. 19% of participants identified as Hispanic/Latino. The mean baseline CD4+ cell count was 663 cells per mm^3 (range 62–2582). Participants were stratified by prior treatment regimen. At screening, 15% of participants were receiving ABC/3TC plus ATV or DRV (given with either cobicistat or ritonavir) and 85% of participants were receiving FTC/TDF plus ATV or DRV (given with either cobicistat or ritonavir).

Treatment outcomes of Trials 1844 and 1878 through Week 48 are presented in Table 15.

Table 15 Virologic Outcomes of Trials 1844 and 1878 at Week 48 [Week 48 window was between Day 295 and 378 (inclusive).] in Virologically-Suppressed Adults who Switched to BIKTARVY
 | Trial 1844 |  | Trial 1878
 | BIKTARVY (N=282) | ABC/DTG/3TC (N=281) | BIKTARVY (N=290) | ATV- or DRV-based regimen [ATV given with cobicistat or ritonavir or DRV given with cobicistat or ritonavir plus either FTC/TDF or ABC/3TC.] (N=287)
HIV-1 RNA ≥ 50 copies/mL [Includes participants who had ≥ 50 copies/mL in the Week 48 window; participants who discontinued early due to lack or loss of efficacy; participants who discontinued for reasons other than lack or loss of efficacy and at the time of discontinuation had a viral value of ≥ 50 copies/mL.] | 1% | <1% | 2% | 2%
Treatment Difference (95% CI) | 0.7% (-1.0% to 2.8%) |  | 0.0% (-2.5% to 2.5%)
HIV-1 RNA < 50 copies/mL | 94% | 95% | 92% | 89%
No Virologic Data at Week 48 Window | 5% | 5% | 6% | 9%
Discontinued Study Drug Due to AE or Death and Last Available HIV-1 RNA < 50 copies/mL | 2% | 1% | 1% | 1%
Discontinued Study Drug Due to Other Reasons and Last Available HIV-1 RNA < 50 copies/mL [Includes participants who discontinued for reasons other than an AE, death, or lack or loss of efficacy, e.g., withdrew consent, loss to follow-up, etc.] | 2% | 3% | 3% | 7%
Missing Data During Window but on Study Drug | 2% | 1% | 2% | 2%

In Trial 1844, treatment outcomes between treatment groups were similar across subgroups by age, sex, race, and region. The mean change from baseline in CD4+ count at Week 48 was -31 cells per mm^3 in participants who switched to BIKTARVY and 4 cells per mm^3 in participants who stayed on ABC/DTG/3TC.

In Trial 1878, treatment outcomes between treatment groups were similar across subgroups by age, sex, race, and region. The mean change from baseline in CD4+ count at Week 48 was 25 cells per mm^3 in patients who switched to BIKTARVY and 0 cells per mm^3 in patients who stayed on their baseline regimen.

In Trial 4030, the efficacy and safety of switching from DTG plus either FTC/TAF or FTC/TDF to BIKTARVY (containing 50 mg of BIC, 200 mg of FTC, and 25 mg of TAF) were evaluated in a randomized, double-blind study of virologically suppressed HIV-1 infected adults. Participants must have been stably suppressed (HIV-1 RNA less than 50 copies/mL) on their baseline regimen for at least 6 months (if documented or suspected NRTI resistance), or at least 3 months (if no documented or suspected NRTI resistance) prior to trial entry. Participants were randomized to switch to BIKTARVY (N=284) or to continue their prior treatment regimen, DTG+ F/TAF (N=281). The primary endpoint was the proportion of participants with HIV-1 RNA ≥ 50 copies/mL at Week 48. At Week 48 the proportion of participants with HIV-1 RNA ≥50 copies/mL was 0.4% (1/284) in the BIKTARVY group and 1.1% (3/281) in the DTG+F/TAF group (difference -0.7% [95%CI: -2.8%, 1.0%]).

Of the participants receiving BIKTARVY, 47 had HIV-1 with pre-existing M184V or I resistance substitutions (M184M/V, M184M/I, M184V/I, M184V) in HIV-1 RT. Eighty-nine percent (42/47) of participants with M184V or I remained suppressed (HIV-1 RNA < 50 copies/mL) and 11% (5/47 participants) did not have virologic data at the Week 48 timepoint due to study drug discontinuation.

In Trial 1825, an open-label single arm trial, the efficacy, safety, and pharmacokinetics of FTC and TAF (components of BIKTARVY) were evaluated in virologically-suppressed adults with ESRD (estimated creatinine clearance of less than 15 mL/min) on chronic hemodialysis treated with FTC+TAF in combination with elvitegravir and cobicistat as a fixed-dose combination tablet for 96 weeks (N=55). In an extension phase of Trial 1825, 10 virologically-suppressed participants switched to BIKTARVY and all participants remained virologically suppressed (HIV-1 RNA < 50 copies/mL) for 48 weeks.

In Trial 4449, the efficacy and safety of switching from a stable antiretroviral regimen to BIKTARVY (containing 50 mg of BIC, 200 mg of FTC, and 25 mg of TAF) were evaluated in an open-label, single arm trial of virologically-suppressed (HIV-1 RNA less than 50 copies per mL) HIV-1 infected adults aged 65 years and over (N=86). Participants treated with BIKTARVY had a mean age of 70 years (range: 65 to 80). The primary endpoint was the proportion of participants with HIV RNA > 50 copies/mL at Week 48. No participants had HIV RNA > 50 copies/mL. Ninety-one percent (78/86) of participants remained suppressed (HIV-1 RNA < 50 copies/mL) at Week 48. Eight participants did not have virologic data at the Week 48 timepoint due to discontinuation or missing data.

14.5 Clinical Trial Results in Pediatric Participants with HIV-1

In Trial 1474, an open-label, single arm trial the efficacy, safety, and pharmacokinetics of BIKTARVY in pediatric participants with HIV-1 were evaluated in virologically-suppressed adolescents between the ages of 12 to less than 18 years weighing at least 35 kg (N=50), in virologically-suppressed children between the ages of 6 to less than 12 years weighing at least 25 kg (N=50), and in virologically-suppressed children at least 2 years of age and weighing at least 14 to less than 25 kg (N=22).

Cohort 1: Virologically-suppressed adolescents (12 to less than 18 years; at least 35 kg)

Participants in cohort 1 treated with BIKTARVY (containing 50 mg of BIC, 200 mg of FTC, and 25 mg of TAF) once daily had a mean age of 14 years (range: 12 to 17) and a mean baseline weight of 51.7 kg (range: 35 to 123), 64% were female, 27% were Asian and 65% were black. At baseline, median CD4+ cell count was 750 cells per mm^3 (range: 337 to 1207), and median CD4+% was 33% (range: 19% to 45%).

After switching to BIKTARVY, 98% (49/50) of participants in cohort 1 remained suppressed (HIV-1 RNA < 50 copies/mL) at Week 48. The mean change from baseline in CD4+ cell count at Week 48 was -22 cells per mm^3.

Cohort 2: Virologically-suppressed children (6 to less than 12 years; at least 25 kg)

Participants in cohort 2 treated with BIKTARVY once daily had a mean age of 10 years (range: 6 to 11) and a mean baseline weight of 31.9 kg (range: 25 to 69), 54% were female, 22% were Asian and 72% were black. At baseline, median CD4+ cell count was 898 cells per mm^3 (range 390 to 1991) and median CD4+% was 37% (range: 19% to 53%).

After switching to BIKTARVY (containing 50 mg of BIC, 200 mg of FTC, and 25 mg of TAF), 100% (50/50) of participants in cohort 2 remained suppressed (HIV-1 RNA < 50 copies/mL) at Week 24. The mean change from baseline in CD4+ cell count at Week 24 was -24 cells per mm^3.

Cohort 3: Virologically-suppressed children (at least 2 years; at least 14 to less than 25 kg)

Participants in cohort 3 treated with BIKTARVY (containing 30 mg of BIC, 120 mg of FTC, and 15 mg of TAF) once daily had a mean age of 5 years (range: 3 to 9) and a mean baseline weight of 18.8 kg (range: 14 to 24), 50% were female, 23% were Asian and 73% were black. At baseline, the mean CD4+ cell count (SD) was 1104 (440), and the mean CD4% (SD) was 33.4% (6.0%).

After switching to BIKTARVY, 91% (20/22) of participants in cohort 3 remained suppressed (HIV-1 RNA < 50 copies/mL) at Week 24. HIV-1 RNA was not collected at Week 24 for 2 participants because of COVID-19 pandemic-related study disruption. The mean change from baseline to Week 24 in CD4+ cell count (SD) was −126 (264.2) cells per mm^3 ; and the mean change in CD4% (SD) from baseline to Week 24 was 0.2% (4.4%).

16 HOW SUPPLIED/STORAGE AND HANDLING

BIKTARVY tablets are available in bottles and blister packs:

Bottle

- 50 mg/200 mg/25 mg tablets each contain 50 mg of bictegravir (BIC), 200 mg of emtricitabine (FTC), and 25 mg of tenofovir alafenamide (TAF). These tablets are purplish brown, capsule-shaped, and film-coated with “GSI” debossed on one side and “9883” on the other side (NDC 61958-2501-1).
- 30 mg/120 mg/15 mg tablets each contain 30 mg of BIC,120 mg of FTC, and 15 mg of TAF. These tablets are pink, capsule-shaped, and film-coated with “GSI” debossed on one side and “B” on the other side (NDC 61958-2505-1).
- 30 mg/120 mg/15 mg tablets each contain 30 mg of BIC,120 mg of FTC, and 15 mg of TAF. These tablets are pink, capsule-shaped, and film-coated with a non- functional bisecting score line on one side and “BVY” on the other side (NDC 61958-2506-1).

Each bottle contains 30 tablets, a silica gel desiccant, polyester coil, and is closed with a child-resistant closure. Do not remove the desiccant packet.

STORAGE AND HANDLING

Store bottle below 30 °C (86 °F).

Keep bottle tightly closed.

Blister Pack

- 50 mg/200 mg/25 mg tablets each contain 50 mg of BIC, 200 mg of FTC, and 25 mg of TAF. These tablets are purplish brown, capsule-shaped, and film-coated with “GSI” debossed on one side and “9883” on the other side (NDC 61958-2501-3).

Each blister pack contains 30 tablets (4 strips each containing 7 tablets and 1 strip containing 2 tablets). Blister packs are sealed with a child-resistant laminated foil lidding material (peel-push), and each blister cavity contains a die-cut desiccant film which is heat staked to the foil lidding material.

STORAGE AND HANDLING

Store blister pack at 25 °C (77 °F), excursions permitted to 15–30 °C (59–86 °F) (see USP Controlled Room Temperature).

Dispense only in original containers.

17 PATIENT COUNSELING INFORMATION

Advise the patient to read the FDA-approved patient labeling (Patient Information).

Post-treatment Acute Exacerbation of Hepatitis B in Participants with HBV

Severe acute exacerbations of hepatitis B have been reported in patients with HBV and HIV-1 who have discontinued products containing FTC and/or TDF, and may likewise occur with discontinuation of BIKTARVY [see Warnings and Precautions (5.1)]. Advise the patient to not discontinue BIKTARVY without first informing their healthcare provider.

Drug Interactions

BIKTARVY may interact with certain drugs; therefore, advise patients to report to their healthcare provider the use of any other prescription or non-prescription medication or herbal products including St. John’s wort [see Contraindications (4) and Drug Interactions (7)].

Immune Reconstitution Syndrome

Advise patients to inform their healthcare provider immediately of any symptoms of infection, as in some patients with advanced HIV infection (AIDS), signs and symptoms of inflammation from previous infections may occur soon after anti-HIV treatment is started [see Warnings and Precautions (5.3)].

Renal Impairment

Advise patients to avoid taking BIKTARVY with concurrent or recent use of nephrotoxic agents. Postmarketing cases of renal impairment, including acute renal failure, have been reported [see Warnings and Precautions (5.4)].

Lactic Acidosis and Severe Hepatomegaly

Lactic acidosis and severe hepatomegaly with steatosis, including fatal cases, have been reported with use of drugs similar to BIKTARVY. Advise patients that they should stop BIKTARVY if they develop clinical symptoms suggestive of lactic acidosis or pronounced hepatotoxicity [see Warnings and Precautions (5.5)].

Missed Dosage

Inform patients that it is important to take BIKTARVY on a regular dosing schedule with or without food and to avoid missing doses as it can result in development of resistance [see Dosage and Administration (2.2)].

Tablet Splitting

Advise caregivers that, for children unable to swallow a whole tablet, the tablet can be split and each part taken separately as long as all parts are ingested within approximately 10 minutes [see Dosage and Administration (2.3)].

Pregnancy Registry

Inform patients that there is an antiretroviral pregnancy registry to monitor fetal outcomes of pregnant individuals exposed to BIKTARVY [see Use in Specific Populations (8.1)].

Lactation

Inform individuals with HIV-1 that the potential risks of breastfeeding include: (1) HIV-1 transmission to infants without HIV-1, (2) developing viral resistance in infants with HIV-1, and (3) adverse reactions in a breastfed infant similar to those seen in adults [see Use in Specific Populations (8.2)].

BIKTARVY is a trademark of Gilead Sciences, Inc., or its related companies. All other trademarks referenced herein are the property of their respective owners.

© 2025 Gilead Sciences, Inc. All rights reserved.

Patient Information
BIKTARVY® (bik-TAR-vee)
(bictegravir, emtricitabine,
and tenofovir alafenamide)
tablets

Important: Ask your healthcare provider or pharmacist about medicines that should not be taken with BIKTARVY. For more information, see “What should I tell my healthcare provider before taking BIKTARVY?”

What is the most important information I should know about BIKTARVY?

BIKTARVY can cause serious side effects, including:

- Worsening of hepatitis B virus (HBV). Your healthcare provider will test you for HBV before or when you start treatment with BIKTARVY. If you have HBV and take BIKTARVY, your HBV may get worse (flare-up) if you stop taking BIKTARVY. A “flare-up” is when your HBV suddenly returns in a worse way than before.
  - Do not run out of BIKTARVY. Refill your prescription or talk to your healthcare provider before your BIKTARVY is all gone.
  - Do not stop taking BIKTARVY without first talking to your healthcare provider.
  - If you stop taking BIKTARVY, your healthcare provider will need to check your health often and do blood tests regularly for several months to check your liver, and may give you a medicine to treat hepatitis B. Tell your healthcare provider about any new or unusual symptoms you may have after you stop taking BIKTARVY.

For more information about side effects, see “What are the possible side effects of BIKTARVY?”

What is BIKTARVY?
BIKTARVY is a prescription medicine that is used without other human immunodeficiency virus-1 (HIV-1) medicines to treat HIV-1 in adults and children who weigh at least 31 pounds (14 kg):

- who have not received HIV-1 medicines in the past, or
- who have received HIV-1 medicines in the past, or to replace their current HIV-1 medicines, and whose healthcare provider determines that they meet certain requirements.

HIV-1 is the virus that causes Acquired Immune Deficiency Syndrome (AIDS).
BIKTARVY contains the medicines bictegravir, emtricitabine, and tenofovir alafenamide.
It is not known if BIKTARVY is safe and effective in children who weigh less than 31 pounds (14 kg).

Do not take BIKTARVY if you also take a medicine that contains:

- dofetilide
- rifampin

What should I tell my healthcare provider before taking BIKTARVY?
Before taking BIKTARVY, tell your healthcare provider about all your medical conditions, including if you:

- have liver problems, including HBV
- have kidney problems
- are pregnant or plan to become pregnant. Tell your healthcare provider if you become pregnant during treatment with BIKTARVY.
  Pregnancy Registry: There is a pregnancy registry for those who take BIKTARVY during pregnancy. The purpose of this registry is to collect information about the health of you and your baby. Talk with your healthcare provider about how you can take part in this registry.
- are breastfeeding or plan to breastfeed. BIKTARVY passes to your baby in your breastmilk. Talk to your healthcare provider about the following risks to your baby from breastfeeding during treatment with BIKTARVY:
  - the HIV-1 virus may pass to your baby if your baby does not have HIV-1.
  - the HIV-1 virus may become harder to treat if your baby has HIV-1.
  - your baby may get side effects from BIKTARVY.

Tell your healthcare provider about all the medicines you take, including prescription and over-the-counter medicines, antacids, laxatives, vitamins, and herbal supplements.
Some medicines may interact with BIKTARVY. Keep a list of your medicines and show it to your healthcare provider and pharmacist when you get a new medicine.

- You can ask your healthcare provider or pharmacist for a list of medicines that interact with BIKTARVY.
- Do not start a new medicine without telling your healthcare provider. Your healthcare provider can tell you if it is safe to take BIKTARVY with other medicines.

How should I take BIKTARVY?

- Take BIKTARVY exactly as your healthcare provider tells you to take it. BIKTARVY is taken by itself (not with other HIV-1 medicines) to treat HIV-1.
- Take BIKTARVY 1 time each day with or without food.
- For children unable to swallow a whole tablet, the tablet can be split and each part taken separately as long as all parts are swallowed within about 10 minutes.
- If you are on dialysis, take your daily dose of BIKTARVY following dialysis.
- Do not change your dose or stop taking BIKTARVY without first talking with your healthcare provider. Stay under a healthcare provider’s care during treatment with BIKTARVY.
- If you take antacids that contain aluminum or magnesium, take BIKTARVY at least 2 hours before or 6 hours after you take these antacids.
- If you take supplements or antacids that contain iron or calcium, take BIKTARVY with food at the same time that you take these supplements or antacids.
- If you are pregnant and take supplements or antacids that contain aluminum, magnesium, iron or calcium, talk to your healthcare provider about how to take BIKTARVY along with these supplements or antacids.
- Do not miss a dose of BIKTARVY.
- If you take too much BIKTARVY, call your healthcare provider or go to the nearest hospital emergency room right away.
- When your BIKTARVY supply starts to run low, get more from your healthcare provider or pharmacy. This is very important because the amount of virus in your blood may increase if the medicine is stopped for even a short time. The virus may develop resistance to BIKTARVY and become harder to treat.

What are the possible side effects of BIKTARVY?

BIKTARVY may cause serious side effects, including:

- See “What is the most important information I should know about BIKTARVY?”
- Changes in your immune system (Immune Reconstitution Syndrome) can happen when you start taking HIV-1 medicines. Your immune system may get stronger and begin to fight infections that have been hidden in your body for a long time. Tell your healthcare provider right away if you start having any new symptoms after starting your HIV-1 medicine.
- New or worse kidney problems, including kidney failure. Your healthcare provider should do blood and urine tests to check your kidneys when starting and during treatment with BIKTARVY. Your healthcare provider may tell you to stop taking BIKTARVY if you develop new or worse kidney problems.
- Too much lactic acid in your blood (lactic acidosis). Too much lactic acid is a serious but rare medical emergency that can lead to death. Tell your healthcare provider right away if you get these symptoms: weakness or being more tired than usual, unusual muscle pain, being short of breath or fast breathing, stomach pain with nausea and vomiting, cold or blue hands and feet, feel dizzy or lightheaded, or a fast or abnormal heartbeat.
- Severe liver problems. In rare cases, severe liver problems can happen that can lead to death. Tell your healthcare provider right away if you get these symptoms: skin or the white part of your eyes turns yellow, dark “tea-colored” urine, light-colored stools, loss of appetite for several days or longer, nausea, or stomach-area pain.

The most common side effects of BIKTARVY are diarrhea, nausea, and headache.

These are not all of the possible side effects of BIKTARVY.

Call your doctor for medical advice about side effects. You may report side effects to FDA at 1-800-FDA-1088.

How should I store BIKTARVY?

- Store BIKTARVY bottle below 86°F (30°C).
- Keep the bottle tightly closed.
- BIKTARVY contains a desiccant packet to help keep your medicine dry (protect it from moisture). Keep the desiccant packet in the bottle. Do not eat the desiccant packet.
- Store BIKTARVY blister pack at room temperature between 68°F to 77°F (20°C to 25°C).
- Keep BIKTARVY in its original bottle or blister pack.
- BIKTARVY comes in a child-resistant package.

Keep BIKTARVY and all medicines out of reach of children.

General information about the safe and effective use of BIKTARVY.

Medicines are sometimes prescribed for purposes other than those listed in a Patient Information leaflet. Do not use BIKTARVY for a condition for which it was not prescribed. Do not give BIKTARVY to other people, even if they have the same symptoms you have. It may harm them. If you would like more information, talk with your healthcare provider. You can ask your healthcare provider or pharmacist for information about BIKTARVY that is written for health professionals.

What are the ingredients in BIKTARVY?

Active ingredients: bictegravir, emtricitabine, and tenofovir alafenamide.

Inactive ingredients: croscarmellose sodium, magnesium stearate, and microcrystalline cellulose.

The tablets are film-coated with a coating material containing iron oxide black, iron oxide red, polyethylene glycol, polyvinyl alcohol, talc, and titanium dioxide.

Manufactured and distributed by: Gilead Sciences, Inc. Foster City, CA 94404

BIKTARVY is a trademark of Gilead Sciences, Inc., or its related companies. All other trademarks referenced herein are the property of their respective owners.

© 2025 Gilead Sciences, Inc. All rights reserved. 210251-GS-015

For more information, call 1-800-445-3235 or go to www.BIKTARVY.com.

This Patient Information has been approved by the U.S. Food and Drug Administration.

Revised:07/2025

PRINCIPAL DISPLAY PANEL - 50 mg/200 mg/25 mg Tablet Bottle Label

NDC 61958-2501-1
30 tablets

Biktarvy ®
(bictegravir, emtricitabine, and
tenofovir alafenamide) tablets
50 mg /200 mg /25 mg

Note to pharmacist:
Do not cover ALERT box with pharmacy label.

ALERT: Find out about medicines that
should NOT be taken with Biktarvy

PRINCIPAL DISPLAY PANEL - 30 mg/120 mg/15 mg Tablet Bottle Label

NDC 61958-2505-1
30 tablets

Biktarvy®
(bictegravir, emtricitabine,
and tenofovir alafenamide)
tablets
30 mg / 120 mg / 15 mg

Note to pharmacist:
Do not cover ALERT box with pharmacy label.

ALERT: Find out about medicines that
should NOT be taken with Biktarvy

PRINCIPAL DISPLAY PANEL - 30 mg/120 mg/15 mg Tablet Bottle Label - NDC 61958-2506

NDC 61958-2506-1
30 tablets

Biktarvy®
(bictegravir, emtricitabine,
and tenofovir alafenamide)
tablets
30 mg / 120 mg / 15 mg

Note to pharmacist:
Do not cover ALERT box with pharmacy label.

ALERT: Find out about medicines that
should NOT be taken with Biktarvy